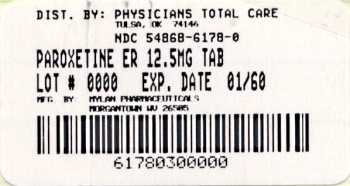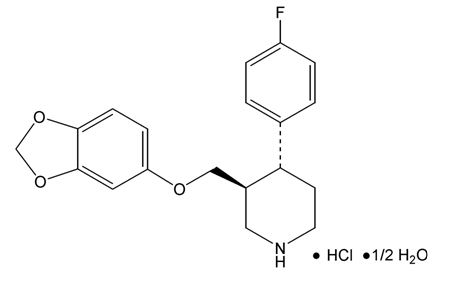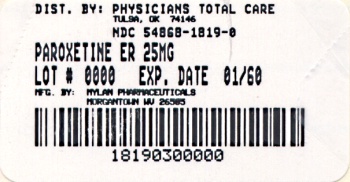 DRUG LABEL: Paroxetine Hydrochloride
NDC: 54868-6178 | Form: TABLET, FILM COATED, EXTENDED RELEASE
Manufacturer: Physicians Total Care, Inc.
Category: prescription | Type: HUMAN PRESCRIPTION DRUG LABEL
Date: 20110517

ACTIVE INGREDIENTS: PAROXETINE HYDROCHLORIDE 12.5 mg/1 1
INACTIVE INGREDIENTS: FERROSOFERRIC OXIDE; SILICON DIOXIDE; HYDROXYPROPYL CELLULOSE; HYPROMELLOSES; LACTOSE MONOHYDRATE; MAGNESIUM STEARATE; METHACRYLIC ACID - ETHYL ACRYLATE COPOLYMER (1:1) TYPE A; CELLULOSE, MICROCRYSTALLINE; POLYDEXTROSE; POLYETHYLENE GLYCOL; POLYSORBATE 80; PROPYLENE GLYCOL; SODIUM HYDROXIDE; TALC; TITANIUM DIOXIDE; TRIACETIN; TRIETHYL CITRATE

Suicidality and Antidepressant Drugs

Antidepressants increased the risk compared to placebo of suicidal thinking and behavior (suicidality) in children, adolescents and young adults in short-term studies of major depressive disorder (MDD) and other psychiatric disorders. Anyone considering the use of paroxetine or any other antidepressant in a child, adolescent or young adult must balance this risk with the clinical need. Short-term studies did not show an increase in the risk of suicidality with antidepressants compared to placebo in adults beyond age 24; there was a reduction in risk with antidepressants compared to placebo in adults aged 65 and older. Depression and certain other psychiatric disorders are themselves associated with increases in the risk of suicide. Patients of all ages who are started on antidepressant therapy should be monitored appropriately and observed closely for clinical worsening, suicidality or unusual changes in behavior. Families and caregivers should be advised of the need for close observation and communication with the prescriber. Paroxetine is not approved for use in pediatric patients. (See WARNINGS: Clinical Worsening and Suicide Risk, PRECAUTIONS: Information for Patients and PRECAUTIONS: Pediatric Use.)

DESCRIPTION

Paroxetine hydrochloride extended-release tablets are an orally administered psychotropic drug with a chemical structure unrelated to other selective serotonin reuptake inhibitors or to tricyclic, tetracyclic or other available antidepressant or antipanic agents. It is the hydrochloride salt of a phenylpiperidine compound identified chemically as (3S-trans)-3-[(1,3-benzodioxol-5-yloxy)methyl)]4-(4-fluorophenyl)-piperidine hydrochloride hemihydrate and has the molecular formula of C19H20FNO3 • HCl • ½ H2O. The molecular weight is 374.8 (329.4 as free base). The structural formula of paroxetine hydrochloride is:

Paroxetine hydrochloride (hemihydrate), USP is an odorless, white to almost white crystalline powder, having a melting point range of 120° to 138°C and a solubility of 5.4 mg/mL in water.

Each enteric film-coated, extended-release tablet contains paroxetine hydrochloride hemihydrate equivalent to 12.5 mg, 25 mg or 37.5 mg paroxetine. Inactive ingredients consist of colloidal silicon dioxide, hydroxypropyl cellulose, hypromellose, lactose monohydrate, magnesium stearate, methacrylic acid copolymer type C, microcrystalline cellulose, polydextrose, polyethylene glycol, polysorbate 80, sodium hydroxide, talc, titanium dioxide, triacetin and triethyl citrate. In addition, the 25 mg product contains the following coloring agents: D&C Red No. 30 Aluminum Lake, FD&C Blue No. 2 Aluminum Lake, FD&C Yellow No. 6 Aluminum Lake and the 37.5 mg product contains D&C Red No. 30 Aluminum Lake, FD&C Yellow No. 6 Aluminum Lake, lecithin and sodium alginate.

In addition, paroxetine hydrochloride extended-release tablets may also contain imprinting ink consisting of either black pigment and natural resin or black iron oxide and propylene glycol.

Paroxetine hydrochloride complies with USP Chromatographic Purity Test 1.

CLINICAL PHARMACOLOGY

Pharmacodynamics

The efficacy of paroxetine in the treatment of major depressive disorder, panic disorder, social anxiety disorder and premenstrual dysphoric disorder (PMDD) is presumed to be linked to potentiation of serotonergic activity in the central nervous system resulting from inhibition of neuronal reuptake of serotonin (5-hydroxy-tryptamine, 5-HT). Studies at clinically relevant doses in humans have demonstrated that paroxetine blocks the uptake of serotonin into human platelets. In vitro studies in animals also suggest that paroxetine is a potent and highly selective inhibitor of neuronal serotonin reuptake and has only very weak effects on norepinephrine and dopamine neuronal reuptake. In vitro radioligand binding studies indicate that paroxetine has little affinity for muscarinic, alpha1-, alpha2-, beta-adrenergic-, dopamine (D2)-, 5-HT1-, 5-HT2- and histamine (H1)-receptors; antagonism of muscarinic, histaminergic and alpha1-adrenergic receptors has been associated with various anticholinergic, sedative and cardiovascular effects for other psychotropic drugs.

Because the relative potencies of paroxetine’s major metabolites are at most 1/50 of the parent compound, they are essentially inactive.

Pharmacokinetics

Paroxetine hydrochloride is completely absorbed after oral dosing of a solution of the hydrochloride salt. The elimination half-life is approximately 15 to 20 hours after a single dose of paroxetine hydrochloride extended-release tablets. Paroxetine is extensively metabolized and the metabolites are considered to be inactive. Nonlinearity in pharmacokinetics is observed with increasing doses. Paroxetine metabolism is mediated in part by CYP2D6 and the metabolites are primarily excreted in the urine and to some extent in the feces. Pharmacokinetic behavior of paroxetine has not been evaluated in subjects who are deficient in CYP2D6 (poor metabolizers).

Absorption and Distribution

Paroxetine hydrochloride is completely absorbed after oral dosing of a solution of the hydrochloride salt. In a study in which normal male and female subjects (n = 23) received single oral doses of paroxetine hydrochloride extended-release tablets at four dosage strengths (12.5 mg, 25 mg, 37.5 mg and 50 mg), paroxetine Cmax and AUC0-inf increased disproportionately with dose (as seen also with immediate-release formulations). Mean Cmax and AUC0-inf values at these doses were 2, 5.5, 9 and 12.5 ng/mL and 121, 261, 338 and 540 ng•hr/mL, respectively. Tmax was observed typically between 6 and 10 hours post-dose, reflecting a reduction in absorption rate compared with immediate-release formulations. The bioavailability of 25 mg paroxetine hydrochloride extended-release tablets is not affected by food.

Paroxetine distributes throughout the body, including the CNS, with only 1% remaining in the plasma.

Approximately 95% and 93% of paroxetine is bound to plasma protein at 100 ng/mL and 400 ng/mL, respectively. Under clinical conditions, paroxetine concentrations would normally be less than 400 ng/mL. Paroxetine does not alter the in vitro protein binding of phenytoin or warfarin.

Metabolism and Excretion

The mean elimination half-life of paroxetine was 15 to 20 hours throughout a range of single doses of paroxetine hydrochloride extended-release tablets (12.5 mg, 25 mg, 37.5 mg and 50 mg). During repeated administration of paroxetine hydrochloride extended-release tablets (25 mg once daily), steady-state was reached within 2 weeks (i.e., comparable to immediate-release formulations). In a repeat dose study in which normal male and female subjects (n = 23) received paroxetine hydrochloride extended-release tablets (25 mg daily), mean steady-state Cmax, Cmin and AUC0-24 values were 30 ng/mL, 20 ng/mL and 550 ng•hr/mL, respectively.

Based on studies using immediate-release formulations, steady-state drug exposure based on AUC0-24 was several-fold greater than would have been predicted from single-dose data. The excess accumulation is a consequence of the fact that one of the enzymes that metabolizes paroxetine is readily saturable.

In steady-state dose proportionality studies involving elderly and nonelderly patients, at doses of the immediate-release formulation of 20 mg to 40 mg daily for the elderly and 20 mg to 50 mg daily for the nonelderly, some nonlinearity was observed in both populations, again reflecting a saturable metabolic pathway. In comparison to Cmin values after 20 mg daily, values after 40 mg daily were only about 2 to 3 times greater than doubled.

Paroxetine is extensively metabolized after oral administration. The principal metabolites are polar and conjugated products of oxidation and methylation, which are readily cleared. Conjugates with glucuronic acid and sulfate predominate and major metabolites have been isolated and identified. Data indicate that the metabolites have no more than 1/50 the potency of the parent compound at inhibiting serotonin uptake. The metabolism of paroxetine is accomplished in part by CYP2D6. Saturation of this enzyme at clinical doses appears to account for the nonlinearity of paroxetine kinetics with increasing dose and increasing duration of treatment. The role of this enzyme in paroxetine metabolism also suggests potential drug-drug interactions (see PRECAUTIONS: Drug Interactions: Drugs Metabolized by CYP2D6).

Approximately 64% of a 30 mg oral solution dose of paroxetine was excreted in the urine with 2% as the parent compound and 62% as metabolites over a 10 day post-dosing period. About 36% was excreted in the feces (probably via the bile), mostly as metabolites and less than 1% as the parent compound over the 10 day post-dosing period.

Other Clinical Pharmacology Information

Specific Populations

Renal and Liver Disease

Increased plasma concentrations of paroxetine occur in subjects with renal and hepatic impairment. The mean plasma concentrations in patients with creatinine clearance below 30 mL/min was approximately 4 times greater than seen in normal volunteers. Patients with creatinine clearance of 30 to 60 mL/min and patients with hepatic functional impairment had about a 2-fold increase in plasma concentrations (AUC, Cmax).

The initial dosage should therefore be reduced in patients with severe renal or hepatic impairment and upward titration, if necessary, should be at increased intervals (see DOSAGE AND ADMINISTRATION).

Elderly Patients

In a multiple-dose study in the elderly at daily doses of 20 mg, 30 mg and 40 mg of the immediate-release formulation, Cmin concentrations were about 70% to 80% greater than the respective Cmin concentrations in nonelderly subjects. Therefore the initial dosage in the elderly should be reduced (see DOSAGE AND ADMINISTRATION).

Drug-Drug Interactions

In vitro drug interaction studies reveal that paroxetine inhibits CYP2D6. Clinical drug interaction studies have been performed with substrates of CYP2D6 and show that paroxetine can inhibit the metabolism of drugs metabolized by CYP2D6 including desipramine, risperidone and atomoxetine (see PRECAUTIONS: Drug Interactions).

Clinical Trials

Major Depressive Disorder

The efficacy of paroxetine hydrochloride extended-release tablets as a treatment for major depressive disorder has been established in two 12 week, flexible dose, placebo-controlled studies of patients with DSM-IV Major Depressive Disorder. One study included patients in the age range 18 to 65 years and a second study included elderly patients, ranging in age from 60 to 88. In both studies, paroxetine hydrochloride extended-release tablets were shown to be significantly more effective than placebo in treating major depressive disorder as measured by the following: Hamilton Depression Rating Scale (HDRS), the Hamilton depressed mood item and the Clinical Global Impression (CGI)–Severity of Illness score.

A study of outpatients with major depressive disorder who had responded to immediate-release paroxetine tablets (HDRS total score < 8) during an initial 8 week open treatment phase and were then randomized to continuation on immediate-release paroxetine tablets or placebo for one year demonstrated a significantly lower relapse rate for patients taking immediate-release paroxetine tablets (15%) compared to those on placebo (39%). Effectiveness was similar for male and female patients.

Panic Disorder

The effectiveness of paroxetine hydrochloride extended-release tablets in the treatment of panic disorder was evaluated in three 10 week, multicenter, flexible dose studies (Studies 1, 2 and 3) comparing paroxetine extended-release tablets (12.5 mg to 75 mg daily) to placebo in adult outpatients who had panic disorder (DSM-IV), with or without agoraphobia. These trials were assessed on the basis of their outcomes on three variables: (1) the proportions of patients free of full panic attacks at endpoint; (2) change from baseline to endpoint in the median number of full panic attacks; and (3) change from baseline to endpoint in the median Clinical Global Impression Severity score. For Studies 1 and 2, paroxetine hydrochloride extended-release tablets were consistently superior to placebo on 2 of these 3 variables. Study 3 failed to consistently demonstrate a significant difference between paroxetine hydrochloride extended-release tablets and placebo on any of these variables.

For all three studies, the mean dose of paroxetine hydrochloride extended-release tablets for completers at endpoint was approximately 50 mg/day. Subgroup analyses did not indicate that there were any differences in treatment outcomes as a function of age or gender.

Long-term maintenance effects of the immediate-release formulation of paroxetine in panic disorder were demonstrated in an extension study. Patients who were responders during a 10 week double-blind phase with immediate-release paroxetine and during a 3 month double-blind extension phase were randomized to either immediate-release paroxetine or placebo in a 3 month double-blind relapse prevention phase. Patients randomized to paroxetine were significantly less likely to relapse than comparably treated patients who were randomized to placebo.

Social Anxiety Disorder

The efficacy of paroxetine hydrochloride extended-release tablets as a treatment for social anxiety disorder has been established, in part, on the basis of extrapolation from the established effectiveness of the immediate-release formulation of paroxetine. In addition, the effectiveness of paroxetine hydrochloride extended-release tablets in the treatment of social anxiety disorder was demonstrated in a 12 week, multicenter, double-blind, flexible dose, placebo-controlled study of adult outpatients with a primary diagnosis of social anxiety disorder (DSM-IV). In the study, the effectiveness of paroxetine hydrochloride extended-release tablets (12.5 mg to 37.5 mg daily) compared to placebo was evaluated on the basis of (1) change from baseline in the Liebowitz Social Anxiety Scale (LSAS) total score and (2) the proportion of responders who scored 1 or 2 (very much improved or much improved) on the Clinical Global Impression (CGI) Global Improvement score.

Paroxetine hydrochloride extended-release tablets demonstrated statistically significant superiority over placebo on both the LSAS total score and the CGI Improvement responder criterion. For patients who completed the trial, 64% of patients treated with paroxetine hydrochloride extended-release tablets compared to 34.7% of patients treated with placebo were CGI Improvement responders.

Subgroup analyses did not indicate that there were any differences in treatment outcomes as a function of gender. Subgroup analyses of studies utilizing the immediate-release formulation of paroxetine generally did not indicate differences in treatment outcomes as a function of age, race or gender.

Premenstrual Dysphoric Disorder

The effectiveness of paroxetine hydrochloride extended-release tablets for the treatment of PMDD utilizing a continuous dosing regimen has been established in two placebo-controlled trials. Patients in these trials met DSM-IV criteria for PMDD. In a pool of 1,030 patients, treated with daily doses of paroxetine hydrochloride extended-release tablets 12.5 or 25 mg/day or placebo the mean duration of the PMDD symptoms was approximately 11 ± 7 years. Patients on systemic hormonal contraceptives were excluded from these trials. Therefore, the efficacy of paroxetine hydrochloride extended-release tablets in combination with systemic (including oral) hormonal contraceptives for the continuous daily treatment of PMDD is unknown. In both positive studies, patients (n = 672) were treated with 12.5 mg/day or 25 mg/day of paroxetine hydrochloride extended-release tablets or placebo continuously throughout the menstrual cycle for a period of 3 menstrual cycles. The VAS-Total score is a patient-rated instrument that mirrors the diagnostic criteria of PMDD as identified in the DSM-IV and includes assessments for mood, physical symptoms and other symptoms. 12.5 mg/day and 25 mg/day of paroxetine hydrochloride extended-release tablets were significantly more effective than placebo as measured by change from baseline to the endpoint on the luteal phase VAS-Total score.

In a third study employing intermittent dosing, patients (n = 366) were treated for the 2 weeks prior to the onset of menses (luteal phase dosing, also known as intermittent dosing) with 12.5 mg/day or 25 mg/day of paroxetine hydrochloride extended-release tablets or placebo for a period of 3 months. 12.5 mg/day and 25 mg/day of paroxetine hydrochloride extended-release tablets, as luteal phase dosing, was significantly more effective than placebo as measured by change from baseline luteal phase VAS total score.

There is insufficient information to determine the effect of race or age on outcome in these studies.

INDICATIONS AND USAGE

Major Depressive Disorder

Paroxetine hydrochloride extended-release tablets are indicated for the treatment of major depressive disorder.

The efficacy of paroxetine hydrochloride extended-release tablets in the treatment of a major depressive episode was established in two 12 week controlled trials of outpatients whose diagnoses corresponded to the DSM-IV category of major depressive disorder (see CLINICAL PHARMACOLOGY: Clinical Trials).

A major depressive episode (DSM-IV) implies a prominent and relatively persistent (nearly every day for at least 2 weeks) depressed mood or loss of interest or pleasure in nearly all activities, representing a change from previous functioning and includes the presence of at least 5 of the following 9 symptoms during the same 2 week period: Depressed mood, markedly diminished interest or pleasure in usual activities, significant change in weight and/or appetite, insomnia or hypersomnia, psychomotor agitation or retardation, increased fatigue, feelings of guilt or worthlessness, slowed thinking or impaired concentration, a suicide attempt or suicidal ideation.

The antidepressant action of paroxetine in hospitalized depressed patients has not been adequately studied.

Paroxetine hydrochloride extended-release tablets have not been systematically evaluated beyond 12 weeks in controlled clinical trials; however, the effectiveness of immediate-release paroxetine hydrochloride in maintaining a response in major depressive disorder for up to one year has been demonstrated in a placebo-controlled trial (see CLINICAL PHARMACOLOGY: Clinical Trials). The physician who elects to use paroxetine hydrochloride extended-release tablets for extended periods should periodically reevaluate the long-term usefulness of the drug for the individual patient (see DOSAGE AND ADMINISTRATION).

Panic Disorder

Paroxetine hydrochloride extended-release tablets are indicated for the treatment of panic disorder, with or without agoraphobia, as defined in DSM-IV. Panic disorder is characterized by the occurrence of unexpected panic attacks and associated concern about having additional attacks, worry about the implications or consequences of the attacks and/or a significant change in behavior related to the attacks.

The efficacy of paroxetine hydrochloride extended-release tablets was established in two 10 week trials in panic disorder patients whose diagnoses corresponded to the DSM-IV category of panic disorder (see CLINICAL PHARMACOLOGY: Clinical Trials).

Panic disorder (DSM-IV) is characterized by recurrent unexpected panic attacks, i.e., a discrete period of intense fear or discomfort in which four (or more) of the following symptoms develop abruptly and reach a peak within 10 minutes: (1) palpitations, pounding heart or accelerated heart rate; (2) sweating; (3) trembling or shaking; (4) sensations of shortness of breath or smothering; (5) feeling of choking; (6) chest pain or discomfort; (7) nausea or abdominal distress; (8) feeling dizzy, unsteady, lightheaded or faint; (9) derealization (feelings of unreality) or depersonalization (being detached from oneself); (10) fear of losing control; (11) fear of dying; (12) paresthesias (numbness or tingling sensations); (13) chills or hot flushes.

Long-term maintenance of efficacy with the immediate-release formulation of paroxetine was demonstrated in a 3 month relapse prevention trial. In this trial, patients with panic disorder assigned to immediate-release paroxetine demonstrated a lower relapse rate compared to patients on placebo (see CLINICAL PHARMACOLOGY: Clinical Trials). Nevertheless, the physician who prescribes paroxetine hydrochloride extended-release tablets for extended periods should periodically reevaluate the long-term usefulness of the drug for the individual patient (see DOSAGE AND ADMINISTRATION).

Social Anxiety Disorder

Paroxetine hydrochloride extended-release tablets are indicated for the treatment of social anxiety disorder, also known as social phobia, as defined in DSM-IV (300.23). Social anxiety disorder is characterized by a marked and persistent fear of one or more social or performance situations in which the person is exposed to unfamiliar people or to possible scrutiny by others. Exposure to the feared situation almost invariably provokes anxiety, which may approach the intensity of a panic attack. The feared situations are avoided or endured with intense anxiety or distress. The avoidance, anxious anticipation or distress in the feared situation(s) interferes significantly with the person's normal routine, occupational or academic functioning or social activities or relationships or there is marked distress about having the phobias. Lesser degrees of performance anxiety or shyness generally do not require psychopharmacological treatment.

The efficacy of paroxetine hydrochloride extended-release tablets as a treatment for social anxiety disorder has been established, in part, on the basis of extrapolation from the established effectiveness of the immediate-release formulation of paroxetine. In addition, the efficacy of paroxetine hydrochloride extended-release tablets was established in a 12 week trial, in adult outpatients with social anxiety disorder (DSM-IV). Paroxetine hydrochloride extended-release tablets have not been studied in children or adolescents with social phobia (see CLINICAL PHARMACOLOGY: Clinical Trials).

The effectiveness of paroxetine hydrochloride extended-release tablets in long-term treatment of social anxiety disorder, i.e., for more than 12 weeks, has not been systematically evaluated in adequate and well controlled trials. Therefore, the physician who elects to prescribe paroxetine hydrochloride extended-release tablets for extended periods should periodically reevaluate the long-term usefulness of the drug for the individual patient (see DOSAGE AND ADMINISTRATION).

Premenstrual Dysphoric Disorder

Paroxetine hydrochloride extended-release tablets are indicated for the treatment of PMDD.

The efficacy of paroxetine hydrochloride extended-release tablets in the treatment of PMDD has been established in 3 placebo-controlled trials (see CLINICAL PHARMACOLOGY: Clinical Trials).

The essential features of PMDD, according to DSM-IV, include markedly depressed mood, anxiety or tension, affective lability and persistent anger or irritability. Other features include decreased interest in usual activities, difficulty concentrating, lack of energy, change in appetite or sleep and feeling out of control. Physical symptoms associated with PMDD include breast tenderness, headache, joint and muscle pain, bloating and weight gain. These symptoms occur regularly during the luteal phase and remit within a few days following the onset of menses; the disturbance markedly interferes with work or school or with usual social activities and relationships with others. In making the diagnosis, care should be taken to rule out other cyclical mood disorders that may be exacerbated by treatment with an antidepressant.

The effectiveness of paroxetine hydrochloride extended-release tablets in long-term use, that is, for more than three menstrual cycles, has not been systematically evaluated in controlled trials. Therefore, the physician who elects to use paroxetine hydrochloride extended-release tablets for extended periods should periodically reevaluate the long-term usefulness of the drug for the individual patient (see DOSAGE AND ADMINISTRATION).

CONTRAINDICATIONS

Paroxetine hydrochloride extended-release tablets should not be used in patients taking monoamine oxidase inhibitors (MAOIs), including linezolid (an antibiotic which is a reversible non-selective MAOI) and methylthioninium chloride (methylene blue) or within 2 weeks of stopping treatment with MAOIs (see WARNINGS).

Concomitant use with thioridazine is contraindicated (see WARNINGS and PRECAUTIONS).

Concomitant use in patients taking pimozide is contraindicated (see PRECAUTIONS).

Paroxetine hydrochloride extended-release tablets are contraindicated in patients with a hypersensitivity to paroxetine or to any of the inactive ingredients in paroxetine hydrochloride extended-release tablets.

WARNINGS

Clinical Worsening and Suicide Risk

Patients with major depressive disorder (MDD), both adult and pediatric, may experience worsening of their depression and/or the emergence of suicidal ideation and behavior (suicidality) or unusual changes in behavior, whether or not they are taking antidepressant medications and this risk may persist until significant remission occurs. Suicide is a known risk of depression and certain other psychiatric disorders and these disorders themselves are the strongest predictors of suicide. There has been a longstanding concern, however, that antidepressants may have a role in inducing worsening of depression and the emergence of suicidality in certain patients during the early phases of treatment. Pooled analyses of short-term placebo-controlled trials of antidepressant drugs (SSRIs and others) showed that these drugs increase the risk of suicidal thinking and behavior (suicidality) in children, adolescents and young adults (ages 18 to 24) with major depressive disorder (MDD) and other psychiatric disorders. Short-term studies did not show an increase in the risk of suicidality with antidepressants compared to placebo in adults beyond age 24; there was a reduction with antidepressants compared to placebo in adults aged 65 and older.

The pooled analyses of placebo-controlled trials in children and adolescents with MDD, obsessive compulsive disorder (OCD) or other psychiatric disorders included a total of 24 short-term trials of nine antidepressant drugs in over 4,400 patients. The pooled analyses of placebo-controlled trials in adults with MDD or other psychiatric disorders included a total of 295 short-term trials (median duration of 2 months) of 11 antidepressant drugs in over 77,000 patients. There was considerable variation in risk of suicidality among drugs, but a tendency toward an increase in the younger patients for almost all drugs studied. There were differences in absolute risk of suicidality across the different indications, with the highest incidence in MDD. The risk differences (drug vs. placebo), however, were relatively stable within age strata and across indications. These risk differences (drug-placebo difference in the number of cases of suicidality per 1,000 patients treated) are provided in Table 1.

Table 1
Age Range | Drug-Placebo Difference in Number of Cases of Suicidality per 1,000 Patients Treated
Increases Compared to Placebo
< 18 | 14 additional cases
18 to 24 | 5 additional cases
Decreases Compared to Placebo
25 to 64 | 1 fewer case
≥ 65 | 6 fewer cases

No suicides occurred in any of the pediatric trials. There were suicides in the adult trials, but the number was not sufficient to reach any conclusion about drug effect on suicide.

It is unknown whether the suicidality risk extends to longer-term use, i.e., beyond several months. However, there is substantial evidence from placebo-controlled maintenance trials in adults with depression that the use of antidepressants can delay the recurrence of depression.

All patients being treated with antidepressants for any indication should be monitored appropriately and observed closely for clinical worsening, suicidality and unusual changes in behavior, especially during the initial few months of a course of drug therapy or at times of dose changes, either increases or decreases.

The following symptoms, anxiety, agitation, panic attacks, insomnia, irritability, hostility, aggressiveness, impulsivity, akathisia (psychomotor restlessness), hypomania and mania, have been reported in adult and pediatric patients being treated with antidepressants for major depressive disorder as well as for other indications, both psychiatric and nonpsychiatric. Although a causal link between the emergence of such symptoms and either the worsening of depression and/or the emergence of suicidal impulses has not been established, there is concern that such symptoms may represent precursors to emerging suicidality.

Consideration should be given to changing the therapeutic regimen, including possibly discontinuing the medication, in patients whose depression is persistently worse or who are experiencing emergent suicidality or symptoms that might be precursors to worsening depression or suicidality, especially if these symptoms are severe, abrupt in onset or were not part of the patient's presenting symptoms.

If the decision has been made to discontinue treatment, medication should be tapered, as rapidly as is feasible, but with recognition that abrupt discontinuation can be associated with certain symptoms (see PRECAUTIONS and DOSAGE AND ADMINISTRATION: Discontinuation of Treatment with Paroxetine Hydrochloride Extended-Release Tablets, for a description of the risks of discontinuation of paroxetine).

Families and caregivers of patients being treated with antidepressants for major depressive disorder or other indications, both psychiatric and nonpsychiatric, should be alerted about the need to monitor patients for the emergence of agitation, irritability, unusual changes in behavior and the other symptoms described above, as well as the emergence of suicidality and to report such symptoms immediately to healthcare providers. Such monitoring should include daily observation by families and caregivers. Prescriptions for paroxetine should be written for the smallest quantity of tablets consistent with good patient management, in order to reduce the risk of overdose.

Screening Patients for Bipolar Disorder

A major depressive episode may be the initial presentation of bipolar disorder. It is generally believed (though not established in controlled trials) that treating such an episode with an antidepressant alone may increase the likelihood of precipitation of a mixed/manic episode in patients at risk for bipolar disorder. Whether any of the symptoms described above represent such a conversion is unknown. However, prior to initiating treatment with an antidepressant, patients with depressive symptoms should be adequately screened to determine if they are at risk for bipolar disorder; such screening should include a detailed psychiatric history, including a family history of suicide, bipolar disorder and depression. It should be noted that paroxetine is not approved for use in treating bipolar depression.

Potential for Interaction With Monoamine Oxidase Inhibitors

In patients receiving another serotonin reuptake inhibitor drug in combination with an MAOI, there have been reports of serious, sometimes fatal, reactions including hyperthermia, rigidity, myoclonus, autonomic instability with possible rapid fluctuations of vital signs and mental status changes that include extreme agitation progressing to delirium and coma. These reactions have also been reported in patients who have recently discontinued that drug and have been started on an MAOI. Some cases presented with features resembling neuroleptic malignant syndrome. While there are no human data showing such an interaction with paroxetine hydrochloride, limited animal data on the effects of combined use of paroxetine and MAOIs suggest that these drugs may act synergistically to elevate blood pressure and evoke behavioral excitation. Therefore, it is recommended that paroxetine hydrochloride extended-release tablets not be used in combination with an MAOI (including linezolid, an antibiotic which is a reversible nonselective MAOI) and methylthioninium chloride [methylene blue] or within 14 days of discontinuing treatment with an MAOI (see CONTRAINDICATIONS). At least 2 weeks should be allowed after stopping paroxetine hydrochloride extended-release tablets before starting an MAOI.

Serotonin Syndrome or Neuroleptic Malignant Syndrome (NMS)-Like Reactions

The development of a potentially life threatening serotonin syndrome or Neuroleptic Malignant Syndrome (NMS)-like reactions have been reported with SNRIs and SSRIs alone, including treatment with paroxetine hydrochloride extended-release tablet, but particularly with concomitant use of serotonergic drugs (including triptans) with drugs which impair metabolism of serotonin (including MAOIs) or with antipsychotics or other dopamine antagonists. Serotonin syndrome symptoms may include mental status changes (e.g., agitation, hallucinations, coma), autonomic instability (e.g., tachycardia, labile blood pressure, hyperthermia), neuromuscular aberrations (e.g., hyperreflexia, incoordination) and/or gastrointestinal symptoms (e.g., nausea, vomiting, diarrhea). Serotonin syndrome, in its most severe form can resemble neuroleptic malignant syndrome, which includes hyperthermia, muscle rigidity, autonomic instability with possible rapid fluctuation of vital signs and mental status changes. Patients should be monitored for the emergence of serotonin syndrome or NMS-like signs and symptoms.

The concomitant use of paroxetine hydrochloride extended-release tablets with MAOIs intended to treat depression is contraindicated.

If concomitant treatment of paroxetine hydrochloride extended-release tablets with a 5-hydroxytryptamine receptor agonist (triptan) is clinically warranted, careful observation of the patient is advised, particularly during treatment initiation and dose increases.

The concomitant use of paroxetine hydrochloride extended-release tablets with serotonin precursors (such as tryptophan) is not recommended.

Treatment with paroxetine hydrochloride extended-release tablets and any concomitant serotonergic or antidopaminergic agents, including antipsychotics, should be discontinued immediately if the above events occur and supportive symptomatic treatment should be initiated.

Potential Interaction with Thioridazine

Thioridazine administration alone produces prolongation of the QTc interval, which is associated with serious ventricular arrhythmias, such as Torsade de pointes type arrhythmias and sudden death. This effect appears to be dose related.

An in vivo study suggests that drugs which inhibit CYP2D6, such as paroxetine, will elevate plasma levels of thioridazine. Therefore, it is recommended that paroxetine not be used in combination with thioridazine (see CONTRAINDICATIONS and PRECAUTIONS).

Usage in Pregnancy

Teratogenic Effects

Epidemiological studies have shown that infants exposed to paroxetine in the first trimester of pregnancy have an increased risk of congenital malformations, particularly cardiovascular malformations. The findings from these studies are summarized below:

- A study based on Swedish national registry data demonstrated that infants exposed to paroxetine during pregnancy (n = 815) had an increased risk of cardiovascular malformations (2% risk in paroxetine-exposed infants) compared to the entire registry population (1% risk), for an odds ratio (OR) of 1.8 (95% confidence interval 1.1 to 2.8). No increase in the risk of overall congenital malformations was seen in the paroxetine-exposed infants. The cardiac malformations in the paroxetine-exposed infants were primarily ventricular septal defects (VSDs) and atrial septal defects (ASDs). Septal defects range in severity from those that resolve spontaneously to those which require surgery.
- A separate retrospective cohort study from the United States (United Healthcare data) evaluated 5,956 infants of mothers dispensed antidepressants during the first trimester (n = 815 for paroxetine). This study showed a trend towards an increased risk for cardiovascular malformations for paroxetine (risk of 1.5%) compared to other antidepressants (risk of 1%), for an OR of 1.5 (95% confidence interval 0.8 to 2.9). Of the 12 paroxetine-exposed infants with cardiovascular malformations, nine had VSDs. This study also suggested an increased risk of overall major congenital malformations including cardiovascular defects for paroxetine (4% risk) compared to other (2% risk) antidepressants (OR 1.8; 95% confidence interval 1.2 to 2.8).
- Two large case control studies using separate databases, each with > 9,000 birth defect cases and > 4,000 controls, found that maternal use of paroxetine during the first trimester of pregnancy was associated with a 2- to 3-fold increased risk of right ventricular outflow tract obstructions. In one study the OR was 2.5 (95% confidence interval, 1 to 6, seven exposed infants) and in the other study the OR was 3.3 (95% confidence interval, 1.3 to 8.8, six exposed infants).

Other studies have found varying results as to whether there was an increased risk of overall, cardiovascular or specific congenital malformations. A meta-analysis of epidemiological data over a 16-year period (1992 to 2008) on first trimester paroxetine use in pregnancy and congenital malformations included the above-noted studies in addition to others (n = 17 studies that included overall malformations and n = 14 studies that included cardiovascular malformations; n = 20 distinct studies). While subject to limitations, this meta-analysis suggested an increased occurrence of cardiovascular malformations (prevalence odds ratio [POR] 1.5; 95% confidence interval 1.2 to 1.9) and overall malformations (POR 1.2; 95% confidence interval 1.1 to 1.4) with paroxetine use during the first trimester. It was not possible in this meta-analysis to determine the extent to which the observed prevalence of cardiovascular malformations might have contributed to that of overall malformations, nor was it possible to determine whether any specific types of cardiovascular malformations might have contributed to the observed prevalence of all cardiovascular malformations.

If a patient becomes pregnant while taking paroxetine, she should be advised of the potential harm to the fetus. Unless the benefits of paroxetine to the mother justify continuing treatment, consideration should be given to either discontinuing paroxetine therapy or switching to another antidepressant (see PRECAUTIONS: Discontinuation of Treatment with Paroxetine Hydrochloride Extended-release Tablets). For women who intend to become pregnant or are in their first trimester of pregnancy, paroxetine should only be initiated after consideration of the other available treatment options.

Animal Findings

Reproduction studies were performed at doses up to 50 mg/kg/day in rats and 6 mg/kg/day in rabbits administered during organogenesis. These doses are approximately 8 (rat) and 2 (rabbit) times the maximum recommended human dose (MRHD) on an mg/m^2 basis. These studies have revealed no evidence of teratogenic effects. However, in rats, there was an increase in pup deaths during the first 4 days of lactation when dosing occurred during the last trimester of gestation and continued throughout lactation. This effect occurred at a dose of 1 mg/kg/day or approximately one-sixth of the MRHD on an mg/m^2 basis. The no effect dose for rat pup mortality was not determined. The cause of these deaths is not known.

Nonteratogenic Effects

Neonates exposed to paroxetine hydrochloride extended-release tablets and other SSRIs or serotonin and norepinephrine reuptake inhibitors (SNRIs), late in the third trimester have developed complications requiring prolonged hospitalization, respiratory support, and tube feeding. Such complications can arise immediately upon delivery. Reported clinical findings have included respiratory distress, cyanosis, apnea, seizures, temperature instability, feeding difficulty, vomiting, hypoglycemia, hypotonia, hypertonia, hyperreflexia, tremor, jitteriness, irritability and constant crying. These features are consistent with either a direct toxic effect of SSRIs and SNRIs or, possibly, a drug discontinuation syndrome. It should be noted that, in some cases, the clinical picture is consistent with serotonin syndrome (see WARNINGS: Serotonin Syndrome or Neuroleptic Malignant Syndrome (NMS)-like Reactions).

Infants exposed to SSRIs in late pregnancy may have an increased risk for persistent pulmonary hypertension of the newborn (PPHN). PPHN occurs in 1 to 2 per 1,000 live births in the general population and is associated with substantial neonatal morbidity and mortality. In a retrospective case control study of 377 women whose infants were born with PPHN and 836 women whose infants were born healthy, the risk for developing PPHN was approximately 6-fold higher for infants exposed to SSRIs after the 20th week of gestation compared to infants who had not been exposed to antidepressants during pregnancy. There is currently no corroborative evidence regarding the risk for PPHN following exposure to SSRIs in pregnancy; this is the first study that has investigated the potential risk. The study did not include enough cases with exposure to individual SSRIs to determine if all SSRIs posed similar levels of PPHN risk.

There have also been post-marketing reports of premature births in pregnant women exposed to paroxetine or other SSRIs.

When treating a pregnant woman with paroxetine during the third trimester, the physician should carefully consider both the potential risks and benefits of treatment (see DOSAGE AND ADMINISTRATION). Physicians should note that in a prospective longitudinal study of 201 women with a history of major depression who were euthymic at the beginning of pregnancy, women who discontinued antidepressant medication during pregnancy were more likely to experience a relapse of major depression than women who continued antidepressant medication.

PRECAUTIONS

General

Activation of Mania/Hypomania

During premarketing testing of immediate-release paroxetine hydrochloride, hypomania or mania occurred in approximately 1% of paroxetine-treated unipolar patients compared to 1.1% of active control and 0.3% of placebo-treated unipolar patients. In a subset of patients classified as bipolar, the rate of manic episodes was 2.2% for immediate-release paroxetine and 11.6% for the combined active control groups. Among 1,627 patients with major depressive disorder, panic disorder, social anxiety disorder or PMDD treated with paroxetine hydrochloride extended-release tablets in controlled clinical studies, there were no reports of mania or hypomania. As with all drugs effective in the treatment of major depressive disorder, paroxetine hydrochloride extended-release tablets should be used cautiously in patients with a history of mania.

Seizures

During premarketing testing of immediate-release paroxetine hydrochloride, seizures occurred in 0.1% of paroxetine-treated patients, a rate similar to that associated with other drugs effective in the treatment of major depressive disorder. Among 1,627 patients who received paroxetine hydrochloride extended-release tablets in controlled clinical trials in major depressive disorder, panic disorder, social anxiety disorder or PMDD, one patient (0.1%) experienced a seizure. Paroxetine hydrochloride extended-release tablets should be used cautiously in patients with a history of seizures. It should be discontinued in any patient who develops seizures.

Discontinuation of Treatment with Paroxetine Hydrochloride Extended-Release Tablets

Adverse events while discontinuing therapy with paroxetine hydrochloride extended-release tablets were not systematically evaluated in most clinical trials; however, in recent placebo-controlled clinical trials utilizing daily doses of paroxetine hydrochloride extended-release tablets up to 37.5 mg/day, spontaneously reported adverse events while discontinuing therapy with paroxetine hydrochloride extended-release tablets were evaluated. Patients receiving 37.5 mg/day underwent an incremental decrease in the daily dose by 12.5 mg/day to a dose of 25 mg/day for one week before treatment was stopped. For patients receiving 25 mg/day or 12.5 mg/day, treatment was stopped without an incremental decrease in dose. With this regimen in those studies, the following adverse events were reported for paroxetine hydrochloride extended-release tablets, at an incidence of 2% or greater for paroxetine hydrochloride extended-release tablets and were at least twice that reported for placebo: Dizziness, nausea, nervousness and additional symptoms described by the investigator as associated with tapering or discontinuing paroxetine hydrochloride extended-release tablets (e.g., emotional lability, headache, agitation, electric shock sensations, fatigue and sleep disturbances). These events were reported as serious in 0.3% of patients who discontinued therapy with paroxetine hydrochloride extended-release tablets.

During marketing of paroxetine hydrochloride extended-release tablets and other SSRIs and SNRIs, there have been spontaneous reports of adverse events occurring upon discontinuation of these drugs, (particularly when abrupt), including the following: Dysphoric mood, irritability, agitation, dizziness, sensory disturbances (e.g., paresthesias such as electric shock sensations and tinnitus), anxiety, confusion, headache, lethargy, emotional lability, insomnia and hypomania. While these events are generally self limiting, there have been reports of serious discontinuation symptoms.

Patients should be monitored for these symptoms when discontinuing treatment with paroxetine hydrochloride extended-release tablets. A gradual reduction in the dose rather than abrupt cessation is recommended whenever possible. If intolerable symptoms occur following a decrease in the dose or upon discontinuation of treatment, then resuming the previously prescribed dose may be considered. Subsequently, the physician may continue decreasing the dose but at a more gradual rate (see DOSAGE AND ADMINISTRATION).

See also PRECAUTIONS: Pediatric Use, for adverse events reported upon discontinuation of treatment with paroxetine in pediatric patients.

Tamoxifen

Some studies have shown that the efficacy of tamoxifen, as measured by the risk of breast cancer relapse/mortality, may be reduced when co-prescribed with paroxetine as a result of paroxetine’s irreversible inhibition of CYP2D6 (see Drug Interactions). However, other studies have failed to demonstrate such a risk. It is uncertain whether the coadministration of paroxetine and tamoxifen has a significant adverse effect on the efficacy of tamoxifen. One study suggests that the risk may increase with longer duration of coadministration. When tamoxifen is used for the treatment or prevention of breast cancer, prescribers should consider using an alternative antidepressant with little or no CYP2D6 inhibition.

Akathisia

The use of paroxetine or other SSRIs has been associated with the development of akathisia, which is characterized by an inner sense of restlessness and psychomotor agitation such as an inability to sit or stand still usually associated with subjective distress. This is most likely to occur within the first few weeks of treatment.

Hyponatremia

Hyponatremia may occur as a result of treatment with SSRIs and SNRIs, including paroxetine hydrochloride extended-release tablets. In many cases, this hyponatremia appears to be the result of the syndrome of inappropriate antidiuretic hormone secretion (SIADH). Cases with serum sodium lower than 110 mmol/L have been reported. Elderly patients may be at greater risk of developing hyponatremia with SSRIs and SNRIs. Also, patients taking diuretics or who are otherwise volume depleted may be at greater risk (see PRECAUTIONS: Geriatric Use). Discontinuation of paroxetine hydrochloride extended-release tablets should be considered in patients with symptomatic hyponatremia and appropriate medical intervention should be instituted.

Signs and symptoms of hyponatremia include headache, difficulty concentrating, memory impairment, confusion, weakness and unsteadiness, which may lead to falls. Signs and symptoms associated with more severe and/or acute cases have included hallucination, syncope, seizure, coma, respiratory arrest and death.

Abnormal Bleeding

SSRIs and SNRIs, including paroxetine, may increase the risk of bleeding events. Concomitant use of aspirin, nonsteroidal anti-inflammatory drugs, warfarin and other anticoagulants may add to this risk. Case reports and epidemiological studies (case control and cohort design) have demonstrated an association between use of drugs that interfere with serotonin reuptake and the occurrence of gastrointestinal bleeding. Bleeding events related to SSRIs and SNRIs use have ranged from ecchymoses, hematomas, epistaxis and petechiae to life threatening hemorrhages. Patients should be cautioned about the risk of bleeding associated with the concomitant use of paroxetine and NSAIDs, aspirin or other drugs that affect coagulation.

Bone Fracture

Epidemiological studies on bone fracture risk following exposure to some antidepressants, including SSRIs, have reported an association between antidepressant treatment and fractures. There are multiple possible causes for this observation and it is unknown to what extent fracture risk is directly attributable to SSRI treatment. The possibility of a pathological fracture, that is, a fracture produced by minimal trauma in a patient with decreased bone mineral density, should be considered in patients treated with paroxetine who present with unexplained bone pain, point tenderness, swelling or bruising.

Use in Patients with Concomitant Illness

Clinical experience with immediate-release paroxetine hydrochloride in patients with certain concomitant systemic illness is limited. Caution is advisable in using paroxetine hydrochloride extended-release tablets in patients with diseases or conditions that could affect metabolism or hemodynamic responses.

As with other SSRIs, mydriasis has been infrequently reported in premarketing studies with paroxetine hydrochloride. A few cases of acute angle closure glaucoma associated with therapy with immediate-release paroxetine have been reported in the literature. As mydriasis can cause acute angle closure in patients with narrow angle glaucoma, caution should be used when paroxetine hydrochloride extended-release tablets are prescribed for patients with narrow angle glaucoma.

Paroxetine hydrochloride extended-release tablets or the immediate-release formulation has not been evaluated or used to any appreciable extent in patients with a recent history of myocardial infarction or unstable heart disease. Patients with these diagnoses were excluded from clinical studies during premarket testing. Evaluation of electrocardiograms of 682 patients who received immediate-release paroxetine hydrochloride in double-blind, placebo-controlled trials, however, did not indicate that paroxetine is associated with the development of significant ECG abnormalities. Similarly, paroxetine hydrochloride does not cause any clinically important changes in heart rate or blood pressure.

Increased plasma concentrations of paroxetine occur in patients with severe renal impairment (creatinine clearance < 30 mL/min.) or severe hepatic impairment. A lower starting dose should be used in such patients (see DOSAGE AND ADMINISTRATION).

Information for Patients

Paroxetine hydrochloride extended-release tablets should not be chewed or crushed and should be swallowed whole.

Patients should be cautioned about the risk of serotonin syndrome with the concomitant use of paroxetine and triptans, tramadol or other serotonergic agents.

Prescribers or other health professionals should inform patients, their families and their caregivers about the benefits and risks associated with treatment with paroxetine and should counsel them in its appropriate use. A patient Medication Guide about “Antidepressant Medicines, Depression and other Serious Mental Illness and Suicidal Thoughts or Actions” is available for paroxetine. The prescriber or health professional should instruct patients, their families and their caregivers to read the Medication Guide and should assist them in understanding its contents. Patients should be given the opportunity to discuss the contents of the Medication Guide and to obtain answers to any questions they may have. The complete text of the Medication Guide is reprinted at the end of this document.

Patients should be advised of the following issues and asked to alert their prescriber if these occur while taking paroxetine.

Clinical Worsening and Suicide Risk

Patients, their families and their caregivers should be encouraged to be alert to the emergence of anxiety, agitation, panic attacks, insomnia, irritability, hostility, aggressiveness, impulsivity, akathisia (psychomotor restlessness), hypomania, mania, other unusual changes in behavior, worsening of depression and suicidal ideation, especially early during antidepressant treatment and when the dose is adjusted up or down. Families and caregivers of patients should be advised to look for the emergence of such symptoms on a day to day basis, since changes may be abrupt. Such symptoms should be reported to the patient's prescriber or health professional, especially if they are severe, abrupt in onset or were not part of the patient's presenting symptoms. Symptoms such as these may be associated with an increased risk for suicidal thinking and behavior and indicate a need for very close monitoring and possibly changes in the medication.

Drugs That Interfere with Hemostasis (e.g., NSAIDs, Aspirin and Warfarin)

Patients should be cautioned about the concomitant use of paroxetine and NSAIDs, aspirin, warfarin or other drugs that affect coagulation since the combined use of psychotropic drugs that interfere with serotonin reuptake and these agents has been associated with an increased risk of bleeding.

Interference with Cognitive and Motor Performance

Any psychoactive drug may impair judgment, thinking or motor skills. Although in controlled studies immediate-release paroxetine hydrochloride has not been shown to impair psychomotor performance, patients should be cautioned about operating hazardous machinery, including automobiles, until they are reasonably certain that therapy with paroxetine hydrochloride extended-release tablets does not affect their ability to engage in such activities.

Completing Course of Therapy

While patients may notice improvement with use of paroxetine hydrochloride extended-release tablets in 1 to 4 weeks, they should be advised to continue therapy as directed.

Concomitant Medications

Patients should be advised to inform their physician if they are taking or plan to take, any prescription or over-the-counter drugs, since there is a potential for interactions.

Alcohol

Although immediate-release paroxetine hydrochloride has not been shown to increase the impairment of mental and motor skills caused by alcohol, patients should be advised to avoid alcohol while taking paroxetine hydrochloride extended-release tablets.

Pregnancy

Patients should be advised to notify their physician if they become pregnant or intend to become pregnant during therapy (see WARNINGS: Usage in Pregnancy: Teratogenic and Nonteratogenic Effects).

Nursing

Patients should be advised to notify their physician if they are breast-feeding an infant (see PRECAUTIONS: Nursing Mothers).

Laboratory Tests

There are no specific laboratory tests recommended.

Drug Interactions

Tryptophan

As with other serotonin reuptake inhibitors, an interaction between paroxetine and tryptophan may occur when they are coadministered. Adverse experiences, consisting primarily of headache, nausea, sweating and dizziness, have been reported when tryptophan was administered to patients taking immediate-release paroxetine. Consequently, concomitant use of paroxetine hydrochloride extended-release tablets with tryptophan is not recommended (see WARNINGS: Serotonin Syndrome or Neuroleptic Malignant Syndrome (NMS)-like Reactions).

Monoamine Oxidase Inhibitors

See CONTRAINDICATIONS and WARNINGS.

Pimozide

In a controlled study of healthy volunteers, after immediate-release paroxetine hydrochloride was titrated to 60 mg daily, coadministration of a single-dose of 2 mg pimozide was associated with mean increases in pimozide AUC of 151% and Cmax of 62%, compared to pimozide administered alone. The increase in pimozide AUC and Cmax is due to the CYP2D6 inhibitory properties of paroxetine. Due to the narrow therapeutic index of pimozide and its known ability to prolong the QT interval, concomitant use of pimozide and paroxetine hydrochloride extended-release tablets are contraindicated (see CONTRAINDICATIONS).

Serotonergic Drugs

Based on the mechanism of action of SNRIs and SSRIs, including paroxetine hydrochloride and the potential for serotonin syndrome, caution is advised when paroxetine hydrochloride extended-release tablets are coadministered with other drugs that may affect the serotonergic neurotransmitter systems, such as triptans, lithium, fentanyl, tramadol or St. John's Wort (see WARNINGS: Serotonin Syndrome or Neuroleptic Malignant Syndrome (NMS)-like Reactions). The concomitant use of paroxetine hydrochloride extended-release tablets with MAOIs (including linezolid and methylene blue) is contraindicated (see CONTRAINDICATIONS). The concomitant use of paroxetine extended-release tablets with other SSRI’s, SNRIs or tryptophan is not recommended (see PRECAUTIONS: Drug Interactions: Trytophan).

Thioridazine

See CONTRAINDICATIONS and WARNINGS.

Warfarin

Preliminary data suggest that there may be a pharmacodynamic interaction (that causes an increased bleeding diathesis in the face of unaltered prothrombin time) between paroxetine and warfarin. Since there is little clinical experience, the concomitant administration of paroxetine hydrochloride extended-release tablets and warfarin should be undertaken with caution (see PRECAUTIONS: Information for Patients: Drugs That Interfere with Hemostasis).

Triptans

There have been rare post-marketing reports of serotonin syndrome with the use of an SSRI and a triptan. If concomitant use of paroxetine hydrochloride extended-release tablets with a triptan is clinically warranted, careful observation of the patient is advised, particularly during treatment initiation and dose increases (see WARNINGS: Serotonin Syndrome or Neuroleptic Malignant Syndrome (NMS)-like Reactions).

Drugs Affecting Hepatic Metabolism

The metabolism and pharmacokinetics of paroxetine may be affected by the induction or inhibition of drug-metabolizing enzymes.

Cimetidine

Cimetidine inhibits many cytochrome P450 (oxidative) enzymes. In a study where immediate-release paroxetine (30 mg once daily) was dosed orally for 4 weeks, steady-state plasma concentrations of paroxetine were increased by approximately 50% during coadministration with oral cimetidine (300 mg three times daily) for the final week. Therefore, when these drugs are administered concurrently, dosage adjustment of paroxetine hydrochloride extended-release tablets after the starting dose should be guided by clinical effect. The effect of paroxetine on cimetidine’s pharmacokinetics was not studied.

Phenobarbital

Phenobarbital induces many cytochrome P450 (oxidative) enzymes. When a single oral 30 mg dose of immediate-release paroxetine was administered at phenobarbital steady-state (100 mg once daily for 14 days), paroxetine AUC and T½ were reduced (by an average of 25% and 38%, respectively) compared to paroxetine administered alone. The effect of paroxetine on phenobarbital pharmacokinetics was not studied. Since paroxetine exhibits nonlinear pharmacokinetics, the results of this study may not address the case where the two drugs are both being chronically dosed. No initial dosage adjustment with paroxetine hydrochloride extended-release tablets is considered necessary when coadministered with phenobarbital; any subsequent adjustment should be guided by clinical effect.

Phenytoin

When a single oral 30 mg dose of immediate-release paroxetine was administered at phenytoin steady-state (300 mg once daily for 14 days), paroxetine AUC and T½ were reduced (by an average of 50% and 35%, respectively) compared to immediate-release paroxetine administered alone. In a separate study, when a single oral 300 mg dose of phenytoin was administered at paroxetine steady-state (30 mg once daily for 14 days), phenytoin AUC was slightly reduced (12% on average) compared to phenytoin administered alone. Since both drugs exhibit nonlinear pharmacokinetics, the above studies may not address the case where the two drugs are both being chronically dosed. No initial dosage adjustments are considered necessary when paroxetine hydrochloride extended-release tablets are coadministered with phenytoin; any subsequent adjustments should be guided by clinical effect (see ADVERSE REACTIONS: Post-marketing Reports).

Drugs Metabolized by CYP2D6

Many drugs, including most drugs effective in the treatment of major depressive disorder (paroxetine, other SSRIs and many tricyclics), are metabolized by the cytochrome P450 isozyme CYP2D6. Like other agents that are metabolized by CYP2D6, paroxetine may significantly inhibit the activity of this isozyme. In most patients (> 90%), this CYP2D6 isozyme is saturated early during paroxetine dosing. In one study, daily dosing of immediate-release paroxetine (20 mg once daily) under steady-state conditions increased single dose desipramine (100 mg) Cmax, AUC and T½ by an average of approximately 2-, 5- and 3-fold, respectively. Concomitant use of paroxetine with risperidone, a CYP2D6 substrate has also been evaluated. In one study, daily dosing of paroxetine 20 mg in patients stabilized on risperidone (4 to 8 mg/day) increased mean plasma concentrations of risperidone approximately 4-fold, decreased 9-hydroxyrisperidone concentrations approximately 10% and increased concentrations of the active moiety (the sum of risperidone plus 9-hydroxyrisperidone) approximately 1.4-fold. The effect of paroxetine on the pharmacokinetics of atomoxetine has been evaluated when both drugs were at steady-state. In healthy volunteers who were extensive metabolizers of CYP2D6, paroxetine 20 mg daily was given in combination with 20 mg atomoxetine every 12 hours. This resulted in increases in steady-state atomoxetine AUC values that were 6- to 8-fold greater and in atomoxetine Cmax values that were 3- to 4-fold greater than when atomoxetine was given alone. Dosage adjustment of atomoxetine may be necessary and it is recommended that atomoxetine be initiated at a reduced dose when given with paroxetine.

Concomitant use of paroxetine hydrochloride extended-release tablets with other drugs metabolized by cytochrome CYP2D6 has not been formally studied but may require lower doses than usually prescribed for either paroxetine hydrochloride extended-release tablets or the other drug.

Therefore, coadministration of paroxetine hydrochloride extended-release tablets with other drugs that are metabolized by this isozyme, including certain drugs effective in the treatment of major depressive disorder (e.g., nortriptyline, amitriptyline, imipramine, desipramine and fluoxetine), phenothiazines, risperidone and Type 1C antiarrhythmics (e.g., propafenone, flecainide and encainide) or that inhibit this enzyme (e.g., quinidine), should be approached with caution.

However, due to the risk of serious ventricular arrhythmias and sudden death potentially associated with elevated plasma levels of thioridazine, paroxetine and thioridazine should not be coadministered (see CONTRAINDICATIONS and WARNINGS).

Tamoxifen is a prodrug requiring metabolic activation by CYP2D6. Inhibition of CYP2D6 by paroxetine may lead to reduced plasma concentrations of an active metabolite (endoxifen) and hence reduced efficacy of tamoxifen (see PRECAUTIONS).

At steady-state, when the CYP2D6 pathway is essentially saturated, paroxetine clearance is governed by alternative P450 isozymes that, unlike CYP2D6, show no evidence of saturation (see PRECAUTIONS: Drug Interactions: Tricyclic Antidepressants (TCAs)).

Drugs Metabolized by Cytochrome CYP3A4

An in vivo interaction study involving the coadministration under steady-state conditions of paroxetine and terfenadine, a substrate for CYP3A4, revealed no effect of paroxetine on terfenadine pharmacokinetics. In addition, in vitro studies have shown ketoconazole, a potent inhibitor of CYP3A4 activity, to be at least 100 times more potent than paroxetine as an inhibitor of the metabolism of several substrates for this enzyme, including terfenadine, astemizole, cisapride, triazolam and cyclosporine. Based on the assumption that the relationship between paroxetine’s in vitro Ki and its lack of effect on terfenadine's in vivo clearance predicts its effect on other CYP3A4 substrates, paroxetine’s extent of inhibition of CYP3A4 activity is not likely to be of clinical significance.

Tricyclic Antidepressants (TCAs)

Caution is indicated in the coadministration of TCAs with paroxetine hydrochloride extended-release tablets, because paroxetine may inhibit TCA metabolism. Plasma TCA concentrations may need to be monitored and the dose of TCA may need to be reduced, if a TCA is coadministered with paroxetine hydrochloride extended-release tablets (see PRECAUTIONS: Drug Interactions: Drugs Metabolized by Cytochrome CYP2D6).

Drugs Highly Bound to Plasma Protein

Because paroxetine is highly bound to plasma protein, administration of paroxetine hydrochloride extended-release tablets to a patient taking another drug that is highly protein bound may cause increased free concentrations of the other drug, potentially resulting in adverse events. Conversely, adverse effects could result from displacement of paroxetine by other highly bound drugs.

Drugs That Interfere with Hemostasis (e.g., NSAIDs, Aspirin and Warfarin)

Serotonin release by platelets plays an important role in hemostasis. Epidemiological studies of the case control and cohort design that have demonstrated an association between use of psychotropic drugs that interfere with serotonin reuptake and the occurrence of upper gastrointestinal bleeding have also shown that concurrent use of an NSAID or aspirin may potentiate this risk of bleeding. Altered anticoagulant effects, including increased bleeding, have been reported when SSRIs or SNRIs are coadministered with warfarin. Patients receiving warfarin therapy should be carefully monitored when paroxetine is initiated or discontinued.

Alcohol

Although paroxetine does not increase the impairment of mental and motor skills caused by alcohol, patients should be advised to avoid alcohol while taking paroxetine hydrochloride extended-release tablets.

Lithium

A multiple-dose study with immediate-release paroxetine hydrochloride has shown that there is no pharmacokinetic interaction between paroxetine and lithium carbonate. However, due to the potential for serotonin syndrome, caution is advised when immediate-release paroxetine hydrochloride is coadministered with lithium.

Digoxin

The steady-state pharmacokinetics of paroxetine was not altered when administered with digoxin at steady-state. Mean digoxin AUC at steady-state decreased by 15% in the presence of paroxetine. Since there is little clinical experience, the concurrent administration of paroxetine hydrochloride extended-release tablets and digoxin should be undertaken with caution.

Diazepam

Under steady-state conditions, diazepam does not appear to affect paroxetine kinetics. The effects of paroxetine on diazepam were not evaluated.

Procyclidine

Daily oral dosing of immediate-release paroxetine (30 mg once daily) increased steady-state AUC0-24, Cmax and Cmin values of procyclidine (5 mg oral once daily) by 35%, 37% and 67%, respectively, compared to procyclidine alone at steady-state. If anticholinergic effects are seen, the dose of procyclidine should be reduced.

Beta-Blockers

In a study where propranolol (80 mg twice daily) was dosed orally for 18 days, the established steady-state plasma concentrations of propranolol were unaltered during coadministration with immediate-release paroxetine (30 mg once daily) for the final 10 days. The effects of propranolol on paroxetine have not been evaluated (see ADVERSE REACTIONS: Post-marketing Reports).

Theophylline

Reports of elevated theophylline levels associated with immediate-release paroxetine treatment have been reported. While this interaction has not been formally studied, it is recommended that theophylline levels be monitored when these drugs are concurrently administered.

Fosamprenavir/Ritonavir

Coadministration of fosamprenavir/ritonavir with paroxetine significantly decreased plasma levels of paroxetine. Any dose adjustment should be guided by clinical effect (tolerability and efficacy).

Electroconvulsive Therapy (ECT)

There are no clinical studies of the combined use of ECT and paroxetine hydrochloride extended-release tablets.

Carcinogenesis, Mutagenesis, Impairment of Fertility

Carcinogenesis

Two year carcinogenicity studies were conducted in rodents given paroxetine in the diet at 1, 5 and 25 mg/kg/day (mice) and 1, 5 and 20 mg/kg/day (rats). These doses are up to approximately 2 (mouse) and 3 (rat) times the (MRHD) on a mg/m^2 basis. There was a significantly greater number of male rats in the high-dose group with reticulum cell sarcomas (1/100, 0/50, 0/50 and 4/50 for control, low-, middle- and high-dose groups, respectively) and a significantly increased linear trend across dose groups for the occurrence of lymphoreticular tumors in male rats. Female rats were not affected. Although there was a dose related increase in the number of tumors in mice, there was no drug-related increase in the number of mice with tumors. The relevance of these findings to humans is unknown.

Mutagenesis

Paroxetine produced no genotoxic effects in a battery of five in vitro and two in vivo assays that included the following: Bacterial mutation assay, mouse lymphoma mutation assay, unscheduled DNA synthesis assay and tests for cytogenetic aberrations in vivo in mouse bone marrow and in vitro in human lymphocytes and in a dominant lethal test in rats.

Impairment of Fertility

Some clinical studies have shown that SSRIs (including paroxetine) may affect sperm quality during SSRI treatment, which may affect fertility in some men.

A reduced pregnancy rate was found in reproduction studies in rats at a dose of paroxetine of 15 mg/kg/day, which is approximately twice the MRHD on a mg/m^2 basis. Irreversible lesions occurred in the reproductive tract of male rats after dosing in toxicity studies for 2 to 52 weeks. These lesions consisted of vacuolation of epididymal tubular epithelium at 50 mg/kg/day and atrophic changes in the seminiferous tubules of the testes with arrested spermatogenesis at 25 mg/kg/day (approximately 8 and 4 times the MRHD on a mg/m^2 basis).

Pregnancy

Pregnancy Category D

See WARNINGS: Usage in Pregnancy: Teratogenic and Nonteratogenic Effects.

Labor and Delivery

The effect of paroxetine on labor and delivery in humans is unknown.

Nursing Mothers

Like many other drugs, paroxetine is secreted in human milk and caution should be exercised when paroxetine hydrochloride extended-release tablets are administered to a nursing woman.

Pediatric Use

Safety and effectiveness in the pediatric population have not been established (see BOX WARNING and WARNINGS: Clinical Worsening and Suicide Risk). Three placebo-controlled trials in 752 pediatric patients with MDD have been conducted with immediate-release paroxetine hydrochloride and the data were not sufficient to support a claim for use in pediatric patients. Anyone considering the use of paroxetine hydrochloride extended-release tablets in a child or adolescent must balance the potential risks with the clinical need. Decreased appetite and weight loss have been observed in association with the use of SSRIs. Consequently, regular monitoring of weight and growth should be performed in children and adolescents treated with an SSRI such as paroxetine hydrochloride extended-release tablets.

In placebo-controlled clinical trials conducted with pediatric patients, the following adverse events were reported in at least 2% of pediatric patients treated with immediate-release paroxetine hydrochloride and occurred at a rate at least twice that for pediatric patients receiving placebo: emotional lability (including self harm, suicidal thoughts, attempted suicide, crying and mood fluctuations), hostility, decreased appetite, tremor, sweating, hyperkinesia and agitation.

Events reported upon discontinuation of treatment with immediate-release paroxetine hydrochloride in the pediatric clinical trials that included a taper phase regimen, which occurred in at least 2% of patients who received immediate-release paroxetine hydrochloride and which occurred at a rate at least twice that of placebo, were: emotional lability (including suicidal ideation, suicide attempt, mood changes and tearfulness), nervousness, dizziness, nausea and abdominal pain (see DOSAGE AND ADMINISTRATION: Discontinuation of Treatment with Paroxetine Hydrochloride Extended-Release Tablets).

Geriatric Use

SSRIs and SNRIs, including paroxetine, have been associated with cases of clinically significant hyponatremia in elderly patients, who may be at greater risk for this adverse event (see PRECAUTIONS: Hyponatremia).

In worldwide premarketing clinical trials with immediate-release paroxetine hydrochloride, 17% of paroxetine-treated patients (approximately 700) were 65 years or older. Pharmacokinetic studies revealed a decreased clearance in the elderly and a lower starting dose is recommended; there were, however, no overall differences in the adverse event profile between elderly and younger patients and effectiveness was similar in younger and older patients (see CLINICAL PHARMACOLOGY and DOSAGE AND ADMINISTRATION).

In a controlled study focusing specifically on elderly patients with major depressive disorder, paroxetine hydrochloride extended-release tablets were demonstrated to be safe and effective in the treatment of elderly patients (> 60 years) with major depressive disorder. (See CLINICAL PHARMACOLOGY: Clinical Trials and ADVERSE REACTIONS: Table 3.)

ADVERSE REACTIONS

The information included under the “Adverse Findings Observed in Short-Term, Placebo-Controlled Trials with Paroxetine Hydrochloride Extended-Release Tablets” subsection of ADVERSE REACTIONS is based on data from eleven placebo-controlled clinical trials. Three of these studies were conducted in patients with major depressive disorder, three studies were done in patients with panic disorder, one study was conducted in patients with social anxiety disorder and four studies were done in female patients with PMDD. Two of the studies in major depressive disorder, which enrolled patients in the age range 18 to 65 years, are pooled. Information from a third study of major depressive disorder, which focused on elderly patients (60 to 88 years), is presented separately as is the information from the panic disorder studies and the information from the PMDD studies. Information on additional adverse events associated with paroxetine hydrochloride extended-release tablets and the immediate-release formulation of paroxetine hydrochloride is included in a separate subsection (see Other Events Observed During the Clinical Development of Paroxetine).

Adverse Findings Observed in Short-Term, Placebo-Controlled Trials With Paroxetine Hydrochloride Extended-Release Tablets

Adverse Events Associated With Discontinuation of Treatment

Major Depressive Disorder

Ten percent (21/212) of patients treated with paroxetine hydrochloride extended-release tablets discontinued treatment due to an adverse event in a pool of two studies of patients with major depressive disorder. The most common events (≥ 1%) associated with discontinuation and considered to be drug-related (i.e., those events associated with dropout at a rate approximately twice or greater for paroxetine hydrochloride extended-release tablets compared to placebo) included the following:

 | Paroxetine Hydrochloride Extended-Release Tablets (n = 212) | Placebo (n = 211)
Nausea | 3.7% | 0.5%
Asthenia | 1.9% | 0.5%
Dizziness | 1.4% | 0%
Somnolence | 1.4% | 0%

In a placebo-controlled study of elderly patients with major depressive disorder, 13% (13/104) of patients treated with paroxetine hydrochloride extended-release tablets discontinued due to an adverse event. Events meeting the above criteria included the following:

 | Paroxetine Hydrochloride Extended-Release Tablets (n = 104) | Placebo (n = 109)
Nausea | 2.9% | 0%
Headache | 1.9% | 0.9%
Depression | 1.9% | 0%
LFT's abnormal | 1.9% | 0%

Panic Disorder

Eleven percent (50/444) of patients treated with paroxetine hydrochloride extended-release tablets in panic disorder studies discontinued treatment due to an adverse event. Events meeting the above criteria included the following:

 | Paroxetine Hydrochloride Extended-Release Tablets (n = 444) | Placebo (n = 445)
Nausea | 2.9% | 0.4%
Insomnia | 1.8% | 0%
Headache | 1.4% | 0.2%
Asthenia | 1.1% | 0%

Social Anxiety Disorder

Three percent (5/186) of patients treated with paroxetine hydrochloride extended-release tablets in the social anxiety disorder study discontinued treatment due to an adverse event. Events meeting the above criteria included the following:

 | Paroxetine Hydrochloride Extended-Release Tablets (n = 186) | Placebo (n = 184)
Nausea | 2.2% | 0.5%
Headache | 1.6% | 0.5%
Diarrhea | 1.1% | 0.5%

Premenstrual Dysphoric Disorder

Spontaneously reported adverse events were monitored in studies of both continuous and intermittent dosing of paroxetine hydrochloride extended-release tablets in the treatment of PMDD. Generally, there were few differences in the adverse event profiles of the two dosing regimens. Thirteen percent (88/681) of patients treated with paroxetine hydrochloride extended-release tablets in PMDD studies of continuous dosing discontinued treatment due to an adverse event.

The most common events (≥ 1%) associated with discontinuation in either group treated with paroxetine hydrochloride extended-release tablets with an incidence rate that is at least twice that of placebo in PMDD trials that employed a continuous dosing regimen are shown in the following table. This table also shows those events that were dose dependent (indicated with an asterisk) as defined as events having an incidence rate with 25 mg of paroxetine hydrochloride extended-release tablets that was at least twice that with 12.5 mg of paroxetine hydrochloride extended-release tablets (as well as the placebo group).

 | Paroxetine Hydrochloride Extended-Release Tablets 25 mg (n = 348) | Paroxetine Hydrochloride Extended-Release Tablets 12.5 mg (n = 333) | Placebo (n = 349)
TOTAL | 15% | 9.9% | 6.3%
Nausea | 6% | 2.4% | 0.9%
Asthenia | 4.9% | 3% | 1.4%
Somnolence* | 4.3% | 1.8% | 0.3%
Insomnia | 2.3% | 1.5% | 0%
Concentration Impaired* | 2% | 0.6% | 0.3%
Dry mouth* | 2% | 0.6% | 0.3%
Dizziness* | 1.7% | 0.6% | 0.6%
Decreased Appetite* | 1.4% | 0.6% | 0%
Sweating* | 1.4% | 0% | 0.3%
Tremor* | 1.4% | 0.3% | 0%
Yawn* | 1.1% | 0% | 0%
Diarrhea | 0.9% | 1.2% | 0%

Commonly Observed Adverse Events

Major Depressive Disorder

The most commonly observed adverse events associated with the use of paroxetine hydrochloride extended-release tablets in a pool of two trials (incidence of 5% or greater and incidence for paroxetine hydrochloride extended-release tablets at least twice that for placebo, derived from Table 2) were: Abnormal ejaculation, abnormal vision, constipation, decreased libido, diarrhea, dizziness, female genital disorders, nausea, somnolence, sweating, trauma, tremor and yawning.

Using the same criteria, the adverse events associated with the use of paroxetine hydrochloride extended-release tablets in a study of elderly patients with major depressive disorder were: Abnormal ejaculation, constipation, decreased appetite, dry mouth, impotence, infection, libido decreased, sweating and tremor.

Panic Disorder

In the pool of panic disorder studies, the adverse events meeting these criteria were: Abnormal ejaculation, somnolence, impotence, libido decreased, tremor, sweating and female genital disorders (generally anorgasmia or difficulty achieving orgasm).

Social Anxiety Disorder

In the social anxiety disorder study, the adverse events meeting these criteria were: Nausea, asthenia, abnormal ejaculation, sweating, somnolence, impotence, insomnia and libido decreased.

Premenstrual Dysphoric Disorder

The most commonly observed adverse events associated with the use of paroxetine hydrochloride extended-release tablets either during continuous dosing or luteal phase dosing (incidence of 5% or greater and incidence for paroxetine hydrochloride extended-release tablets at least twice that for placebo, derived from Table 6) were: Nausea, asthenia, libido decreased, somnolence, insomnia, female genital disorders, sweating, dizziness, diarrhea and constipation.

In the luteal phase dosing PMDD trial, which employed dosing of 12.5 mg/day or 25 mg/day of paroxetine hydrochloride extended-release tablets limited to the 2 weeks prior to the onset of menses over 3 consecutive menstrual cycles, adverse events were evaluated during the first 14 days of each off-drug phase. When the three off-drug phases were combined, the following adverse events were reported at an incidence of 2% or greater for paroxetine hydrochloride extended-release tablets and were at least twice the rate of that reported for placebo: Infection (5.3% versus 2.5%), depression (2.8% versus 0.8%), insomnia (2.4% versus 0.8%), sinusitis (2.4% versus 0%) and asthenia (2% versus 0.8%).

Incidence in Controlled Clinical Trials

Table 2 enumerates adverse events that occurred at an incidence of 1% or more among patients treated with paroxetine hydrochloride extended-release tablets, aged 18 to 65, who participated in two short-term (12 week) placebo-controlled trials in major depressive disorder in which patients were dosed in a range of 25 mg to 62.5 mg/day. Table 3 enumerates adverse events reported at an incidence of 5% or greater among elderly patients (ages 60 to 88) treated with paroxetine hydrochloride extended-release tablets who participated in a short-term (12 week) placebo-controlled trial in major depressive disorder in which patients were dosed in a range of 12.5 mg to 50 mg/day. Table 4 enumerates adverse events reported at an incidence of 1% or greater among patients (19 to 72 years) treated with paroxetine hydrochloride extended-release tablets who participated in short-term (10 week) placebo-controlled trials in panic disorder in which patients were dosed in a range of 12.5 mg to 75 mg/day. Table 5 enumerates adverse events reported at an incidence of 1% or greater among adult patients treated with paroxetine hydrochloride extended-release tablets who participated in a short-term (12 week), double-blind, placebo-controlled trial in social anxiety disorder in which patients were dosed in a range of 12.5 to 37.5 mg/day. Table 6 enumerates adverse events that occurred at an incidence of 1% or more among patients treated with paroxetine hydrochloride extended-release tablets who participated in three, 12-week, placebo-controlled trials in PMDD in which patients were dosed at 12.5 mg/day or 25 mg/day and in one 12-week placebo-controlled trial in which patients were dosed for 2 weeks prior to the onset of menses (luteal phase dosing) at 12.5 mg/day or 25 mg/day. Reported adverse events were classified using a standard COSTART-based Dictionary terminology.

The prescriber should be aware that these figures cannot be used to predict the incidence of side effects in the course of usual medical practice where patient characteristics and other factors differ from those that prevailed in the clinical trials. Similarly, the cited frequencies cannot be compared with figures obtained from other clinical investigations involving different treatments, uses and investigators. The cited figures, however, do provide the prescribing physician with some basis for estimating the relative contribution of drug and nondrug factors to the side effect incidence rate in the population studied.

Table 2. Treatment Emergent Adverse Events Occurring in ≥1% of Patients Treated with Paroxetine Hydrochloride Extended-Release Tablets in a Pool of Two Studies in Major Depressive Disorder
Body System/Adverse Event | % Reporting Event
Body System/Adverse Event | Paroxetine Hydrochloride Extended-Release Tablets (n = 212) | Placebo (n = 211)
Body as a Whole
Headache | 27% | 20%
Asthenia | 14% | 9%
Infection | 8% | 5%
Abdominal Pain | 7% | 4%
Back Pain | 5% | 3%
Trauma | 5% | 1%
Pain | 3% | 1%
Allergic Reaction | 2% | 1%
Cardiovascular System
Tachycardia | 1% | 0%
Vasodilatation | 2% | 0%
Digestive System
Nausea | 22% | 10%
Diarrhea | 18% | 7%
Dry Mouth | 15% | 8%
Constipation | 10% | 4%
Flatulence | 6% | 4%
Decreased Appetite | 4% | 2%
Vomiting | 2% | 1%
Nervous System
Somnolence | 22% | 8%
Insomnia | 17% | 9%
Dizziness | 14% | 4%
Libido Decreased | 7% | 3%
Tremor | 7% | 1%
Hypertonia | 3% | 1%
Paresthesia | 3% | 1%
Agitation | 2% | 1%
Confusion | 1% | 0%
Respiratory System
Yawn | 5% | 0%
Rhinitis | 4% | 1%
Cough Increased | 2% | 1%
Bronchitis | 1% | 0%
Skin and Appendages
Sweating | 6% | 2%
Photosensitivity | 2% | 0%
Special Senses
Abnormal Vision | 5% | 1%
Taste Perversion | 2% | 0%
Urogenital System
Abnormal Ejaculation | 26% | 1%
Female Genital Disorderà | 10% | <1%
Impotenceà | 5% | 3%
Urinary Tract Infection | 3% | 1%
Menstrual Disorderà | 2% | <1%
Vaginitisà | 2% | 0%

Table 3. Treatment Emergent Adverse Events Occurring in ≥ 5% of Patients Treated with Paroxetine Hydrochloride Extended-Release Tablets in a Study of Elderly Patients with Major Depressive Disorder
Body System/Adverse Event | % Reporting Event
Body System/Adverse Event | Paroxetine Hydrochloride Extended-Release Tablets (n = 104) | Placebo (n = 109)
Body as a Whole
Headache | 17% | 13%
Asthenia | 15% | 14%
Trauma | 8% | 5%
Infection | 6% | 2%
Digestive System
Dry Mouth | 18% | 7%
Diarrhea | 15% | 9%
Constipation | 13% | 5%
Dyspepsia | 13% | 10%
Decreased Appetite | 12% | 5%
Flatulence | 8% | 7%
Nervous System
Somnolence | 21% | 12%
Insomnia | 10% | 8%
Dizziness | 9% | 5%
Libido Decreased | 8% | <1%
Tremor | 7% | 0%
Skin and Appendages
Sweating | 10% | <1%
Urogenital System
Abnormal Ejaculation | 17% | 3%
Impotence‡ | 9% | 3%

Table 4. Treatment Emergent Adverse Events Occurring in ≥ 1% of Patients Treated with Paroxetine Hydrochloride Extended-Release Tablets in a Pool of Three Panic Disorder Studies
Body System/Adverse Event | % Reporting Event
Body System/Adverse Event | Paroxetine Hydrochloride Extended-Release Tablets (n = 444) | Placebo (n = 445)
Body as a Whole
Asthenia | 15% | 10%
Abdominal Pain | 6% | 4%
Trauma | 5% | 4%
Cardiovascular System
Vasodilation | 3% | 2%
Digestive System
Nausea | 23% | 17%
Dry Mouth | 13% | 9%
Diarrhea | 12% | 9%
Constipation | 9% | 6%
Decreased Appetite | 8% | 6%
Metabolic/Nutritional Disorders
Weight Loss | 1% | 0%
Musculoskeletal System
Myalgia | 5% | 3%
Nervous System
Insomnia | 20% | 11%
Somnolence | 20% | 9%
Libido Decreased | 9% | 4%
Nervousness | 8% | 7%
Tremor | 8% | 2%
Anxiety | 5% | 4%
Agitation | 3% | 2%
Hypertonia | 2% | <1%
Myoclonus | 2% | <1%
Respiratory System
Sinusitis | 8% | 5%
Yawn | 3% | 0%
Skin and Appendages
Sweating | 7% | 2%
Special Senses
Abnormal Vision | 3% | <1%
Urogenital System
Abnormal Ejaculation | 27% | 3%
ImpotenceÞ | 10% | 1%
Female Genital Disorders | 7% | 1%
Urinary Frequency | 2% | <1%
Urination Impaired | 2% | <1%
Vaginitisà | 1% | <1%

Table 5. Treatment Emergent Adverse Effects Occurring in ≥ 1% of Patients Treated with Paroxetine Hydrochloride Extended-Release Tablets in a Social Anxiety Disorder Study
Body System/Adverse Event | % Reporting Event
Body System/Adverse Event | Paroxetine Hydrochloride Extended-Release Tablets (n = 186) | Placebo (n = 184)
Body as a Whole
Headache | 23% | 17%
Asthenia | 18% | 7%
Abdominal Pain | 5% | 4%
Back Pain | 4% | 1%
Trauma | 3% | <1%
Allergic Reaction | 2% | <1%
Chest Pain | 1% | <1%
Cardiovascular System
Hypertension | 2% | 0%
Migraine | 2% | 1%
Tachycardia | 2% | 1%
Digestive System
Nausea | 22% | 6%
Diarrhea | 9% | 8%
Constipation | 5% | 2%
Dry Mouth | 3% | 2%
Dyspepsia | 2% | <1%
Decreased Appetite | 1% | <1%
Tooth Disorder | 1% | 0%
Metabolic/Nutritional Disorders
Weight Gain | 3% | 1%
Weight Loss | 1% | 0%
Nervous System
Insomnia | 9% | 4%
Somnolence | 9% | 4%
Libido Decreased | 8% | 1%
Dizziness | 7% | 4%
Tremor | 4% | 2%
Anxiety | 2% | 1%
Concentration Impaired | 2% | 0%
Depression | 2% | 1%
Myoclonus | 1% | <1%
Paresthesia | 1% | <1%
Respiratory System
Yawn | 2% | 0%
Skin and Appendages
Sweating | 14% | 3%
Eczema | 1% | 0%
Special Senses
Abnormal Vision | 2% | 0%
Abnormality of Accommodation | 2% | 0%
Urogenital System
Abnormal Ejaculation | 15% | 1%
Impotence# | 9% | 0%
Female Genital Disorders | 3% | 0%

Table 6. Treatment-Emergent Adverse Events Occurring in > 1% of Patients Treated With Paroxetine Hydrochloride Extended-Release Tablets in a Pool of Three Premenstrual Dysphoric Disorder Studies with Continuous Dosing or in One Premenstrual Dysphoric Disorder Study with Luteal Phase Dosing
Body System/Adverse Event | % Reporting Event
Body System/Adverse Event | Continuous Dosing |  | Luteal Phase Dosing
Body System/Adverse Event | Paroxetine Hydrochloride Extended-Release Tablets (n = 681) | Placebo (n = 349) | Paroxetine Hydrochloride Extended-Release Tablets (n = 246) | Placebo (n = 120)
Body as a Whole
Asthenia | 17% | 6% | 15% | 4%
Headache | 15% | 12% | - | -
Infection | 6% | 4% | - | -
Abdominal pain | - | - | 3% | 0%
Cardiovascular System
Migraine | 1% | < 1% | - | -
Digestive System
Nausea | 17% | 7% | 18% | 2%
Diarrhea | 6% | 2% | 6% | 0%
Constipation | 5% | 1% | 2% | < 1%
Dry Mouth | 4% | 2% | 2% | < 1%
Increased Appetite | 3% | < 1% | - | -
Decreased Appetite | 2% | < 1% | 2% | 0%
Dyspepsia | 2% | 1% | 2% | 2%
Gingivitis | - | - | 1% | 0%
Metabolic and Nutritional Disorders
Generalized Edema | - | - | 1% | < 1%
Weight Gain | - | - | 1% | < 1%
Musculoskeletal System
Arthralgia | 2% | 1% | - | -
Nervous System
Libido Decreased | 12% | 5% | 9% | 6%
Somnolence | 9% | 2% | 3% | < 1%
Insomnia | 8% | 2% | 7% | 3%
Dizziness | 7% | 3% | 6% | 3%
Tremor | 4% | < 1% | 5% | 0%
Concentration Impaired | 3% | < 1% | 1% | 0%
Nervousness | 2% | < 1% | 3% | 2%
Anxiety | 2% | 1% | - | -
Lack of Emotion | 2% | < 1% | - | -
Depression | - | - | 2% | < 1%
Vertigo | - | - | 2% | < 1%
Abnormal Dreams | < 1% | < 1% | - | -
Amnesia | - | - | 1% | 0%
Respiratory System
Sinusitis | - | - | 4% | 2%
Yawn | 2% | < 1% | - | -
Bronchitis | - | - | 2% | 0%
Cough Increased | 1% | < 1% | - | -
Skin and Appendages
Sweating | 7% | < 1% | 6% | < 1%
Special Senses
Abnormal Vision | - | - | 1% | 0%
Urogenital System
Female Genital Disorders | 8% | 1% | 2% | 0%
Menorrhagia | 1% | < 1% | - | -
Vaginal Moniliasis | 1% | < 1% | - | -
Menstrual Disorder | - | - | 1% | 0%

Dose Dependency of Adverse Events

The following table shows results in PMDD trials of common adverse events, defined as events with an incidence of ≥ 1% with 25 mg of paroxetine hydrochloride extended release tablets that was at least twice that with 12.5 mg of paroxetine hydrochloride extended release tablets and with placebo.

Table 7. Incidence of Common Adverse Events in Placebo, 12.5 mg and 25 mg of Paroxetine Hydrochloride Extended-release Tablets in a Pool of Three Fixed-Dose PMDD Trials
 | Paroxetine Hydrochloride Extended-Release Tablets 25 mg (n = 348) | Paroxetine Hydrochloride Extended-Release Tablets 12.5 mg (n = 333) | Placebo (n = 349)
Common Adverse Event
Sweating | 8.9% | 4.2% | 0.9%
Tremor | 6% | 1.5% | 0.3%
Concentration Impaired | 4.3% | 1.5% | 0.6%
Yawn | 3.2% | 0.9% | 0.3%
Paresthesia | 1.4% | 0.3% | 0.3%
Hyperkinesia | 1.1% | 0.3% | 0%
Vaginitis | 1.1% | 0.3% | 0.3%

A comparison of adverse event rates in a fixed dose study comparing immediate-release paroxetine with placebo in the treatment of major depressive disorder revealed a clear dose dependency for some of the more common adverse events associated with the use of immediate-release paroxetine.

Male and Female Sexual Dysfunction with SSRIs

Although changes in sexual desire, sexual performance and sexual satisfaction often occur as manifestations of a psychiatric disorder, they may also be a consequence of pharmacologic treatment. In particular, some evidence suggests that SSRIs can cause such untoward sexual experiences.

Reliable estimates of the incidence and severity of untoward experiences involving sexual desire, performance and satisfaction are difficult to obtain; however, in part because patients and physicians may be reluctant to discuss them. Accordingly, estimates of the incidence of untoward sexual experience and performance cited in product labeling, are likely to underestimate their actual incidence.

The percentage of patients reporting symptoms of sexual dysfunction in the pool of two placebo-controlled trials in nonelderly patients with major depressive disorder, in the pool of three placebo-controlled trials in patients with panic disorder, in the placebo-controlled trial in patients with social anxiety disorder and in the intermittent dosing and the pool of three placebo-controlled continuous dosing trials in female patients with PMDD are as follows:

 | Major Depressive Disorder |  | Panic Disorder |  | Social Anxiety Disorder |  | PMDD Continuous Dosing |  | PMDD Luteal Phase Dosing
 | Paroxetine HCl Extended- Release Tablets | Placebo | Paroxetine HCl Extended- Release Tablets | Placebo | Paroxetine HCl Extended- Release Tablets | Placebo | Paroxetine HCl Extended- Release Tablets | Placebo | Paroxetine HCl Extended- Release Tablets | Placebo
n (males) | 78 | 78 | 162 | 194 | 88 | 97 | n/a | n/a | n/a | n/a
Decreased Libido | 10% | 5% | 9% | 6% | 13% | 1% | n/a | n/a | n/a | n/a
Ejaculatory Disturbance | 26% | 1% | 27% | 3% | 15% | 1% | n/a | n/a | n/a | n/a
Impotence | 5% | 3% | 10% | 1% | 9% | 0% | n/a | n/a | n/a | n/a
n (females) | 134 | 133 | 282 | 251 | 98 | 87 | 681 | 349 | 246 | 120
Decreased Libido | 4% | 2% | 8% | 2% | 4% | 1% | 12% | 5% | 9% | 6%
Orgasmic Disturbance | 10% | <1% | 7% | 1% | 3% | 0% | 8% | 1% | 2% | 0%

There are no adequate, controlled studies examining sexual dysfunction with paroxetine treatment.

Paroxetine treatment has been associated with several cases of priapism. In those cases with a known outcome, patients recovered without sequelae.

While it is difficult to know the precise risk of sexual dysfunction associated with the use of SSRIs, physicians should routinely inquire about such possible side effects.

Weight and Vital Sign Changes

Significant weight loss may be an undesirable result of treatment with paroxetine for some patients but, on average, patients in controlled trials with paroxetine hydrochloride extended-release tablets or the immediate-release formulation, had minimal weight loss (about 1 pound). No significant changes in vital signs (systolic and diastolic blood pressure, pulse and temperature) were observed in patients treated with paroxetine hydrochloride extended-release tablets or immediate-release paroxetine hydrochloride, in controlled clinical trials.

ECG Changes

In an analysis of ECGs obtained in 682 patients treated with immediate-release paroxetine and 415 patients treated with placebo in controlled clinical trials, no clinically significant changes were seen in the ECGs of either group.

Liver Function Tests

In a pool of two placebo-controlled clinical trials, patients treated with paroxetine hydrochloride extended-release tablets or placebo exhibited abnormal values on liver function tests at comparable rates. In particular, the extended-release paroxetine versus placebo comparisons for alkaline phosphatase, SGOT, SGPT and bilirubin revealed no differences in the percentage of patients with marked abnormalities.

In a study of elderly patients with major depressive disorder, 3 of 104 patients treated with paroxetine hydrochloride extended-release tablets and none of 109 placebo patients experienced liver transaminase elevations of potential clinical concern.

Two of the patients treated with paroxetine hydrochloride extended-release tablets dropped out of the study due to abnormal liver function tests; the third patient experienced normalization of transaminase levels with continued treatment. Also, in the pool of three studies of patients with panic disorder, 4 of 444 patients treated with paroxetine hydrochloride extended-release tablets and none of 445 placebo patients experienced liver transaminase elevations of potential clinical concern. Elevations in all four patients decreased substantially after discontinuation of paroxetine hydrochloride extended-release tablets. The clinical significance of these findings is unknown.

In placebo-controlled clinical trials with the immediate-release formulation of paroxetine, patients exhibited abnormal values on liver function tests at no greater rate than that seen in placebo-treated patients.

Hallucinations

In pooled clinical trials of immediate-release paroxetine hydrochloride, hallucinations were observed in 22 of 9,089 patients receiving drug and in 4 of 3,187 patients receiving placebo.

Other Events Observed During the Clinical Development of Paroxetine

The following adverse events were reported during the clinical development of paroxetine hydrochloride extended-release tablets and/or the clinical development of the immediate-release formulation of paroxetine.

Adverse events for which frequencies are provided below occurred in clinical trials with the extended-release formulation of paroxetine. During its premarketing assessment in major depressive disorder, panic disorder, social anxiety disorder and PMDD, multiple doses of paroxetine hydrochloride extended-release tablets were administered to 1,627 patients in phase three double-blind, controlled, outpatient studies. Untoward events associated with this exposure were recorded by clinical investigators using terminology of their own choosing. Consequently, it is not possible to provide a meaningful estimate of the proportion of individuals experiencing adverse events without first grouping similar types of untoward events into a smaller number of standardized event categories.

In the tabulations that follow, reported adverse events were classified using a COSTART based dictionary. The frequencies presented, therefore, represent the proportion of the 1,627 patients exposed to paroxetine hydrochloride extended-release tablets who experienced an event of the type cited on at least one occasion while receiving paroxetine hydrochloride extended-release tablets. All reported events are included except those already listed in Tables 2 through 7 and those events where a drug cause was remote. If the COSTART term for an event was so general as to be uninformative, it was deleted or, when possible, replaced with a more informative term. It is important to emphasize that although the events reported occurred during treatment with paroxetine, they were not necessarily caused by it.

Events are further categorized by body system and listed in order of decreasing frequency according to the following definitions: Frequent adverse events are those occurring on one or more occasions in at least 1/100 patients (only those not already listed in the tabulated results from placebo-controlled trials appear in this listing); infrequent adverse events are those occurring in 1/100 to 1/1,000 patients; rare events are those occurring in fewer than 1/1,000 patients.

Adverse events for which frequencies are not provided occurred during the premarketing assessment of immediate-release paroxetine in phase two and three studies of major depressive disorder, obsessive compulsive disorder, panic disorder, social anxiety disorder, generalized anxiety disorder and posttraumatic stress disorder. The conditions and duration of exposure to immediate-release paroxetine varied greatly and included (in overlapping categories) open and double-blind studies, uncontrolled and controlled studies, inpatient and outpatient studies and fixed dose and titration studies. Only those events not previously listed for extended-release paroxetine are included. The extent to which these events may be associated with paroxetine hydrochloride extended-release tablets is unknown.

Events are listed alphabetically within the respective body system. Events of major clinical importance are also described in the PRECAUTIONS section.

Body as a Whole: Infrequent were chills, face edema, fever, flu syndrome, malaise; rare were abscess, anaphylactoid reaction, anticholinergic syndrome, hypothermia; also observed were adrenergic syndrome, neck rigidity, sepsis.

Cardiovascular System: Infrequent were angina pectoris, bradycardia, hematoma, hypertension, hypotension, palpitation, postural hypotension, supraventricular tachycardia, syncope; rare were bundle branch block; also observed were arrhythmia nodal, atrial fibrillation, cerebrovascular accident, congestive heart failure, low cardiac output, myocardial infarct, myocardial ischemia, pallor, phlebitis, pulmonary embolus, supraventricular extrasystoles, thrombophlebitis, thrombosis, vascular headache, ventricular extrasystoles.

Digestive System: Infrequent were bruxism, dysphagia, eructation, gastritis, gastroenteritis, gastroesophageal reflux, gingivitis, hemorrhoids, liver function test abnormal, melena, pancreatitis, rectal hemorrhage, toothache, ulcerative stomatitis; rare were colitis, glossitis, gum hyperplasia, hepatosplenomegaly, increased salivation, intestinal obstruction, peptic ulcer, stomach ulcer, throat tightness; also observed were aphthous stomatitis, bloody diarrhea, bulimia, cardiospasm, cholelithiasis, duodenitis, enteritis, esophagitis, fecal impactions, fecal incontinence, gum hemorrhage, hematemesis, hepatitis, ileitis, ileus, jaundice, mouth ulceration, salivary gland enlargement, sialadenitis, stomatitis, tongue discoloration, tongue edema.

Endocrine System: Infrequent were ovarian cyst, testes pain; rare were diabetes mellitus, hyperthyroidism; also observed were goiter, hypothyroidism, thyroiditis.

Hemic and Lymphatic System: Infrequent were anemia, eosinophilia, hypochromic anemia, leukocytosis, leukopenia, lymphadenopathy, purpura; rare were thrombocytopenia; also observed were anisocytosis, basophilia, bleeding time increased, lymphedema, lymphocytosis, lymphopenia, microcytic anemia, monocytosis, normocytic anemia, thrombocythemia.

Metabolic and Nutritional Disorders: Infrequent were generalized edema, hyperglycemia, hypokalemia, peripheral edema, SGOT increased, SGPT increased, thirst; rare were bilirubinemia, dehydration, hyperkalemia, obesity; also observed were alkaline phosphatase increased, BUN increased, creatinine phosphokinase increased, gamma globulins increased, gout, hypercalcemia, hypercholesteremia, hyperphosphatemia, hypocalcemia, hypoglycemia, hyponatremia, ketosis, lactic dehydrogenase increased, nonprotein nitrogen (NPN) increased.

Musculoskeletal System: Infrequent were arthritis, bursitis, tendonitis; rare were myasthenia, myopathy, myositis; also observed were generalized spasm, osteoporosis, tenosynovitis, tetany.

Nervous System: Frequent were depression; infrequent were amnesia, convulsion, depersonalization, dystonia, emotional lability, hallucinations, hyperkinesia, hypesthesia, hypokinesia, incoordination, libido increased, neuralgia, neuropathy, nystagmus, paralysis, vertigo; rare were ataxia, coma, diplopia, dyskinesia, hostility, paranoid reaction, torticollis, withdrawal syndrome; also observed were abnormal gait, akathisia, akinesia, aphasia, choreoathetosis, circumoral paresthesia, delirium, delusions, dysarthria, euphoria, extrapyramidal syndrome, fasciculations, grand mal convulsion, hyperalgesia, irritability, manic reaction, manic-depressive reaction, meningitis, myelitis, peripheral neuritis, psychosis, psychotic depression, reflexes decreased, reflexes increased, stupor, trismus.

Respiratory System: Frequent were pharyngitis; infrequent were asthma, dyspnea, epistaxis, laryngitis, pneumonia; rare were stridor; also observed were dysphonia, emphysema, hemoptysis, hiccups, hyperventilation, lung fibrosis, pulmonary edema, respiratory flu, sputum increased.

Skin and Appendages: Frequent were rash; infrequent were acne, alopecia, dry skin, eczema, pruritus, urticaria; rare were exfoliative dermatitis, furunculosis, pustular rash, seborrhea; also observed were angioedema, ecchymosis, erythema multiforme, erythema nodosum, hirsutism, maculopapular rash, skin discoloration, skin hypertrophy, skin ulcer, sweating decreased, vesiculobullous rash.

Special Senses: Infrequent were conjunctivitis, earache, keratoconjunctivitis, mydriasis, photophobia, retinal hemorrhage, tinnitus; rare were blepharitis, visual field defect; also observed were amblyopia, anisocoria, blurred vision, cataract, conjunctival edema, corneal ulcer, deafness, exophthalmos, glaucoma, hyperacusis, night blindness, parosmia, ptosis, taste loss.

Urogenital System: Frequent were dysmenorrhea^1; infrequent were albuminuria, amenorrhea^1, breast pain^1, cystitis, dysuria, prostatitis^1, urinary retention; rare were breast enlargement^1, breast neoplasm^1, female lactation, hematuria, kidney calculus, metrorrhagia^1, nephritis, nocturia, pregnancy and puerperal disorders^1, salpingitis, urinary incontinence, uterine fibroids enlarged; also observed were breast atrophy, ejaculatory disturbance, endometrial disorder, epididymitis, fibrocystic breast, leukorrhea, mastitis, oliguria, polyuria, pyuria, urethritis, urinary casts, urinary urgency, urolith, uterine spasm, vaginal hemorrhage.

Post-Marketing Reports

Voluntary reports of adverse events in patients taking immediate-release paroxetine hydrochloride that have been received since market introduction and not listed above that may have no causal relationship with the drug include acute pancreatitis, elevated liver function tests (the most severe cases were deaths due to liver necrosis and grossly elevated transaminases associated with severe liver dysfunction), Guillain-Barré syndrome, Stevens-Johnson syndrome, toxic epidermal necrolysis, priapism, syndrome of inappropriate ADH secretion, symptoms suggestive of prolactinemia and galactorrhea; extrapyramidal symptoms which have included akathisia, bradykinesia, cogwheel rigidity, dystonia, hypertonia, oculogyric crisis which has been associated with concomitant use of pimozide; tremor and trismus; status epilepticus, acute renal failure, pulmonary hypertension, allergic alveolitis, anaphylaxis, eclampsia, laryngismus, optic neuritis, porphyria, restless leg syndrome (RLS), ventricular fibrillation, ventricular tachycardia (including Torsade de pointes), thrombocytopenia, hemolytic anemia, events related to impaired hematopoiesis (including aplastic anemia, pancytopenia, bone marrow aplasia and agranulocytosis) and vasculitic syndromes (such as Henoch-Schönlein purpura). There has been a case report of an elevated phenytoin level after 4 weeks of immediate-release paroxetine and phenytoin coadministration. There has been a case report of severe hypotension when immediate-release paroxetine was added to chronic metoprolol treatment.

DRUG ABUSE AND DEPENDENCE

Controlled Substance Class

Paroxetine hydrochloride is not a controlled substance.

Physical and Psychologic Dependence

Paroxetine hydrochloride extended-release tablets have not been systematically studied in animals or humans for its potential for abuse, tolerance or physical dependence. While the clinical trials did not reveal any tendency for any drug seeking behavior, these observations were not systematic and it is not possible to predict on the basis of this limited experience the extent to which a CNS active drug will be misused, diverted and/or abused once marketed. Consequently, patients should be evaluated carefully for history of drug abuse and such patients should be observed closely for signs of misuse or abuse of paroxetine hydrochloride extended-release tablets (e.g., development of tolerance, incrementations of dose, drug seeking behavior).

OVERDOSAGE

Human Experience

Since the introduction of immediate-release paroxetine hydrochloride in the United States, 342 spontaneous cases of deliberate or accidental overdosage during paroxetine treatment have been reported worldwide (circa 1999). These include overdoses with paroxetine alone and in combination with other substances. Of these, 48 cases were fatal and of the fatalities, 17 appeared to involve paroxetine alone. Eight fatal cases that documented the amount of paroxetine ingested were generally confounded by the ingestion of other drugs or alcohol or the presence of significant comorbid conditions. Of 145 nonfatal cases with known outcome, most recovered without sequelae. The largest known ingestion involved 2000 mg of paroxetine (33 times the maximum recommended daily dose) in a patient who recovered.

Commonly reported adverse events associated with paroxetine overdosage include somnolence, coma, nausea, tremor, tachycardia, confusion, vomiting and dizziness. Other notable signs and symptoms observed with overdoses involving paroxetine (alone or with other substances) include mydriasis, convulsions (including status epilepticus), ventricular dysrhythmias (including Torsade de pointes), hypertension, aggressive reactions, syncope, hypotension, stupor, bradycardia, dystonia, rhabdomyolysis, symptoms of hepatic dysfunction (including hepatic failure, hepatic necrosis, jaundice, hepatitis and hepatic steatosis), serotonin syndrome, manic reactions, myoclonus, acute renal failure and urinary retention.

Overdosage Management

No specific antidotes for paroxetine are known. Treatment should consist of those general measures employed in the management of overdosage with any drugs effective in the treatment of major depressive disorder.

Ensure an adequate airway, oxygenation and ventilation. Monitor cardiac rhythm and vital signs. General supportive and symptomatic measures are also recommended. Induction of emesis is not recommended. Due to the large volume of distribution of this drug, forced diruesis, dialysis, hemoperfusion or exchange perfusion are unlikely to be of benefit.

A specific caution involves patients taking or recently having taken paroxetine who might ingest excessive quantities of a tricyclic antidepressant. In such a case, accumulation of the parent tricyclic and an active metabolite may increase the possibility of clinically significant sequelae and extend the time needed for close medical observation (see PRECAUTIONS: Drug Interactions: Drugs Metabolized by Cytochrome CPY2D6).

In managing overdosage, consider the possibility of multiple drug involvement. The physician should consider contacting a poison control center for additional information on the treatment of any overdose. Telephone numbers for certified poison control centers are listed in the Physicians' Desk Reference (PDR).

Dosages referenced in the DOSAGE AND ADMINISTRATION section below are in terms of paroxetine rather than paroxetine hydrochloride.

DOSAGE AND ADMINISTRATION

Major Depressive Disorder

Usual Initial Dosage

Paroxetine hydrochloride extended-release tablets should be administered as a single daily dose, usually in the morning, with or without food. The recommended initial dose is 25 mg/day. Patients were dosed in a range of 25 mg to 62.5 mg/day in the clinical trials demonstrating the effectiveness of paroxetine hydrochloride extended-release tablets in the treatment of major depressive disorder. As with all drugs effective in the treatment of major depressive disorder, the full effect may be delayed. Some patients not responding to a 25 mg dose may benefit from dose increases, in 12.5 mg/day increments, up to a maximum of 62.5 mg/day. Dose changes should occur at intervals of at least one week.

Patients should be cautioned that paroxetine hydrochloride extended-release tablets should not be chewed or crushed and should be swallowed whole.

Maintenance Therapy

There is no body of evidence available to answer the question of how long the patient treated with paroxetine hydrochloride extended-release tablets should remain on it. It is generally agreed that acute episodes of major depressive disorder require several months or longer of sustained pharmacologic therapy. Whether the dose of an antidepressant needed to induce remission is identical to the dose needed to maintain and/or sustain euthymia is unknown.

Systematic evaluation of the efficacy of immediate-release paroxetine hydrochloride has shown that efficacy is maintained for periods of up to one year with doses that averaged about 30 mg, which corresponds to a 37.5 mg dose of paroxetine hydrochloride extended-release tablets, based on relative bioavailability considerations (see CLINICAL PHARMACOLOGY).

Panic Disorder

Usual Initial Dosage

Paroxetine hydrochloride extended-release tablets should be administered as a single daily dose, usually in the morning. Patients should be started on 12.5 mg/day. Dose changes should occur in 12.5 mg/day increments and at intervals of at least one week. Patients were dosed in a range of 12.5 to 75 mg/day in the clinical trials demonstrating the effectiveness of paroxetine hydrochloride extended-release tablets. The maximum dosage should not exceed 75 mg/day.

Patients should be cautioned that paroxetine hydrochloride extended-release tablets should not be chewed or crushed and should be swallowed whole.

Maintenance Therapy

Long-term maintenance of efficacy with the immediate-release formulation of paroxetine was demonstrated in a 3 month relapse prevention trial. In this trial, patients with panic disorder assigned to immediate-release paroxetine demonstrated a lower relapse rate compared to patients on placebo. Panic disorder is a chronic condition and it is reasonable to consider continuation for a responding patient. Dosage adjustments should be made to maintain the patient on the lowest effective dosage and patients should be periodically reassessed to determine the need for continued treatment.

Social Anxiety Disorder

Usual Initial Dosage

Paroxetine hydrochloride extended-release tablets should be administered as a single daily dose, usually in the morning, with or without food. The recommended initial dose is 12.5 mg/day. Patients were dosed in a range of 12.5 mg to 37.5 mg/day in the clinical trial demonstrating the effectiveness of paroxetine hydrochloride extended-release tablets in the treatment of social anxiety disorder. If the dose is increased, this should occur at intervals of at least one week, in increments of 12.5 mg/day, up to a maximum of 37.5 mg/day.

Patients should be cautioned that paroxetine hydrochloride extended-release tablets should not be chewed or crushed and should be swallowed whole.

Maintenance Therapy

There is no body of evidence available to answer the question of how long the patient treated with paroxetine hydrochloride extended-release tablets should remain on it. Although the efficacy of paroxetine hydrochloride extended-release tablets beyond 12 weeks of dosing has not been demonstrated in controlled clinical trials, social anxiety disorder is recognized as a chronic condition and it is reasonable to consider continuation of treatment for a responding patient. Dosage adjustments should be made to maintain the patient on the lowest effective dosage and patients should be periodically reassessed to determine the need for continued treatment.

Premenstrual Dysphoric Disorder

Usual Initial Dosage

Paroxetine hydrochloride extended-release tablets should be administered as a single daily dose, usually in the morning, with or without food. Paroxetine hydrochloride extended-release tablets may be administered either daily throughout the menstrual cycle or limited to the luteal phase of the menstrual cycle, depending on physician assessment. The recommended initial dose is 12.5 mg/day. In clinical trials, both 12.5 mg/day and 25 mg/day were shown to be effective. Dose changes should occur at intervals of at least one week.

Patients should be cautioned that paroxetine hydrochloride extended-release tablets should not be chewed or crushed and should be swallowed whole.

Maintenance/Continuation Therapy

The effectiveness of paroxetine hydrochloride extended-release tablets for a period exceeding three menstrual cycles has not been systematically evaluated in controlled trials. However, women commonly report that symptoms worsen with age until relieved by the onset of menopause. Therefore, it is reasonable to consider continuation of a responding patient. Patients should be periodically reassessed to determine the need for continued treatment.

Special Populations

Treatment of Pregnant Women During the Third Trimester

Neonates exposed to paroxetine hydrochloride extended-release tablets and other SSRIs or SNRIs, late in the third trimester have developed complications requiring prolonged hospitalization, respiratory support and tube feeding (see WARNINGS: Usage in Pregnancy). When treating pregnant women with paroxetine during the third trimester, the physician should carefully consider the potential risks and benefits of treatment. The physician may consider tapering paroxetine in the third trimester.

Dosage for Elderly or Debilitated Patients and Patients with Severe Renal or Hepatic Impairment

The recommended initial dose of paroxetine hydrochloride extended-release tablets is 12.5 mg/day for elderly patients, debilitated patients and/or patients with severe renal or hepatic impairment. Increases may be made if indicated. Dosage should not exceed 50 mg/day.

Switching Patients to or From a Monoamine Oxidase Inhibitor

At least 14 days should elapse between discontinuation of an MAOI and initiation of therapy with paroxetine hydrochloride extended-release tablets. Similarly, at least 14 days should be allowed after stopping paroxetine hydrochloride extended-release tablets before starting an MAOI.

Discontinuation of Treatment with Paroxetine Hydrochloride Extended-Release Tablets

Symptoms associated with discontinuation of immediate-release paroxetine hydrochloride or paroxetine hydrochloride extended-release tablets have been reported (see PRECAUTIONS: General: Discontinuation of Treatment with Paroxetine Hydrochloride Extended-release Tablets). Patients should be monitored for these symptoms when discontinuing treatment, regardless of the indication for which paroxetine hydrochloride extended-release tablets are being prescribed. A gradual reduction in the dose rather than abrupt cessation is recommended whenever possible. If intolerable symptoms occur following a decrease in the dose or upon discontinuation of treatment, then resuming the previously prescribed dose may be considered. Subsequently, the physician may continue decreasing the dose but at a more gradual rate.

HOW SUPPLIED

Paroxetine Hydrochloride Extended-release Tablets are available containing paroxetine hydrochloride (hemihydrate) USP, equivalent to 12.5 mg, 25 mg paroxetine.

The 12.5 mg tablet is a white enteric film-coated, round, unscored tablet with M over P3 imprinted in black ink on one side of the tablet and blank on the other side. They are available as follows:

Bottles of 30 | NDC 54868-6178-0

The 25 mg tablet is a lavender enteric film-coated, round, unscored tablet with M over P4 imprinted in black ink on one side of the tablet and blank on the other side. They are available as follows:

Bottles of 30 | NDC 54868-1819-0

Store at 20° to 25 °C (68° to 77°F). [See USP Controlled Room Temperature.]

Dispense in a tight, light-resistant container as defined in the USP using a child-resistant closure.

PHARMACIST: Dispense a Medication Guide with each prescription.

MEDICATION GUIDE
PAROXETINE HYDROCHLORIDE EXTENDED-RELEASE TABLETS
(pa rox′ e teen hye″ droe klor′ ide)
12.5 mg, 25 mg and 37.5 mg

Read the Medication Guide that comes with paroxetine hydrochloride extended-release tablets before you start taking it and each time you get a refill. There may be new information. This Medication Guide does not take the place of talking to your healthcare provider about your medical condition or treatment. Talk with your healthcare provider if there is something you do not understand or want to learn more about.

What is the most important information I should know about paroxetine hydrochloride extended-release tablets?

Paroxetine hydrochloride extended-release tablets and other antidepressant medicines may cause serious side effects, including:

1. Suicidal thoughts or actions:
  - Paroxetine hydrochloride extended-release tablets and other antidepressant medicines may increase suicidal thoughts or actions in some children, teenagers or young adults within the first few months of treatment or when the dose is changed.
  - Depression or other serious mental illnesses are the most important causes of suicidal thoughts or actions.
  - Watch for these changes and call your healthcare provider right away if you notice:
    - New or sudden changes in mood, behavior, actions, thoughts or feelings, especially if severe.
    - Pay particular attention to such changes when paroxetine hydrochloride extended-release tablets are started or when the dose is changed.
  Keep all follow-up visits with your healthcare provider and call between visits if you are worried about symptoms.
  Call your healthcare provider right away if you have any of the following symptoms or call 911 if an emergency, especially if they are new, worse or worry you:
  - attempts to commit suicide
  - acting on dangerous impulses
  - acting aggressive or violent
  - thoughts about suicide or dying
  - new or worse depression
  - new or worse anxiety or panic attacks
  - feeling agitated, restless, angry or irritable
  - trouble sleeping
  - an increase in activity or talking more than what is normal for you
  - other unusual changes in behavior or mood
  Call your healthcare provider right away if you have any of the following symptoms or call 911 if an emergency. Paroxetine hydrochloride extended-release tablets may be associated with these serious side effects:
2. Serotonin Syndrome or Neuroleptic Malignant Syndrome-like reactions. This condition can be life threatening and may include:
  - agitation, hallucinations, coma or other changes in mental status
  - coordination problems or muscle twitching (overactive reflexes)
  - racing heartbeat, high or low blood pressure
  - sweating or fever
  - nausea, vomiting or diarrhea
  - muscle rigidity
3. Severe allergic reactions:
  - trouble breathing
  - swelling of the face, tongue, eyes or mouth
  - rash, itchy welts (hives) or blisters, alone or with fever or joint pain
4. Abnormal bleeding: Paroxetine hydrochloride extended-release tablets and other antidepressant medicines may increase your risk of bleeding or bruising, especially if you take the blood thinner warfarin (Coumadin®*, Jantoven®*), a non-steroidal anti-inflammatory drug (NSAIDs, like ibuprofen or naproxen) or aspirin.
5. Seizures or convulsions
6. Manic episodes:
  - greatly increased energy
  - severe trouble sleeping
  - racing thoughts
  - reckless behavior
  - unusually grand ideas
  - excessive happiness or irritability
  - talking more or faster than usual
7. Changes in appetite or weight. Children and adolescents should have height and weight monitored during treatment.
8. Low salt (sodium) levels in the blood. Elderly people may be at greater risk for this. Symptoms may include:
  - headache
  - weakness or feeling unsteady
  - confusion, problems concentrating or thinking or memory problems

Do not stop paroxetine hydrochloride extended-release tablets without first talking to your healthcare provider.

Stopping paroxetine hydrochloride extended-release tablets too quickly may cause serious symptoms including:

- anxiety, irritability, high or low mood, feeling restless or changes in sleep habits
- headache, sweating, nausea, dizziness
- electric shock-like sensations, shaking, confusion

What are paroxetine hydrochloride extended-release tablets?

Paroxetine hydrochloride extended-release tablets are a prescription medicine used to treat depression. It is important to talk with your healthcare provider about the risks of treating depression and also the risks of not treating it. You should discuss all treatment choices with your healthcare provider. Paroxetine hydrochloride extended-release tablets are also used to treat:

- Major Depressive Disorder (MDD)
- Panic Disorder
- Social Anxiety Disorder
- Premenstrual Dysphoric Disorder

Talk to your healthcare provider if you do not think that your condition is getting better with treatment using paroxetine hydrochloride extended-release tablets.

Who should not take paroxetine hydrochloride extended-release tablets?

Do not take paroxetine hydrochloride extended-release tablets if you:

- are allergic to paroxetine hydrochloride or any of the ingredients in paroxetine hydrochloride extended-release tablets. See the end of this Medication Guide for a complete list of ingredients in paroxetine hydrochloride extended-release tablets.
- take a Monoamine Oxidase Inhibitor (MAOI), such as PARNATE®* (tranylcypromine), NARDIL®* (phenelzine) or the antibiotic ZYVOX®* (linezolid). Ask your healthcare provider or pharmacist if you are not sure if you take an MAOI.
  - Do not take an MAOI within 2 weeks of stopping paroxetine hydrochloride extended-release tablets.
  - Do not start paroxetine hydrochloride extended-release tablets if you stopped taking an MAOI in the last 2 weeks.
  - People who take paroxetine hydrochloride extended-release tablets close in time to an MAOI may have serious or even life threatening side effects. Get medical help right away if you have any of these symptoms:
    - high fever
    - uncontrolled muscle spasms
    - stiff muscles
    - rapid changes in heart rate or blood pressure
    - confusion
    - loss of consciousness (pass out)
  - take MELLARIL®* (thioridazine). Do not take MELLARIL®* together with paroxetine hydrochloride extended-release tablets because this can cause serious heart rhythm problems or sudden death.
  - take the antipsychotic medicine pimozide (ORAP®*) because this can cause serious heart problems.

What should I tell my healthcare provider before taking paroxetine hydrochloride extended-release tablets? Ask if you are not sure.

Before starting paroxetine hydrochloride extended-release tablets, tell your healthcare provider if you:

- are pregnant, may be pregnant or plan to become pregnant. There is a possibility that paroxetine hydrochloride extended-release tablets may harm your unborn baby, including an increased risk of birth defects, particularly heart defects. Other risks may include a serious condition in which there is not enough oxygen in the baby’s blood. Your baby may also have certain other symptoms shortly after birth. Premature births have also been reported in some women who used paroxetine hydrochloride extended-release tablets during pregnancy.
- are breast-feeding. Paroxetine passes into your milk. Talk to your healthcare provider about the best way to feed your baby while taking paroxetine hydrochloride extended-release tablets.
- are taking certain drugs such as:
  - triptans used to treat migraine headache
  - other antidepressants (SSRIs, SNRIs, tricyclics or lithium) or antipsychotics
  - drugs that affect serotonin, such as lithium, tramadol, tryptophan, St. John’s wort
  - certain drugs used to treat irregular heart beats
  - certain drugs used to treat schizophrenia
  - certain drugs used to treat HIV infection
  - certain drugs that affect the blood, such as warfarin, aspirin and ibuprofen
  - certain drugs used to treat epilepsy
  - atomoxetine
  - cimetidine
  - fentanyl
  - metoprolol
  - pimozide
  - procyclidine
  - tamoxifen
- have liver problems
- have kidney problems
- have heart problems
- have or had seizures or convulsions
- have bipolar disorder or mania
- have low sodium levels in your blood
- have a history of a stroke
- have high blood pressure
- have or had bleeding problems
- have glaucoma (high pressure in the eye)

Tell your healthcare provider about all the medicines you take, including prescription and non-prescription medicines, vitamins and herbal supplements. Paroxetine hydrochloride extended-release tablets and some medicines may interact with each other, may not work as well or may cause serious side effects.

Your healthcare provider or pharmacist can tell you if it is safe to take paroxetine hydrochloride extended-release tablets with your other medicines. Do not start or stop any medicine while taking paroxetine hydrochloride extended-release tablets without talking to your healthcare provider first.

BOXED WARNING

If you take paroxetine hydrochloride extended-release tablets, you should not take any other medicines that contain paroxetine hydrochloride, including paroxetine tablets and PEXEVA®* (paroxetine mesylate).

How should I take paroxetine hydrochloride extended-release tablets?

- Take paroxetine hydrochloride extended-release tablets exactly as prescribed. Your healthcare provider may need to change the dose of paroxetine hydrochloride extended-release tablets until it is the right dose for you.
- Paroxetine hydrochloride extended-release tablets may be taken with or without food.
- Paroxetine hydrochloride extended-release tablets should not be chewed or crushed and should be swallowed whole.
- If you miss a dose of paroxetine hydrochloride extended-release tablets, take the missed dose as soon as you remember. If it is almost time for the next dose, skip the missed dose and take your next dose at the regular time. Do not take two doses of paroxetine hydrochloride extended-release tablets at the same time.
- If you take too much paroxetine, call your healthcare provider or poison control center right away or get emergency treatment.
- Do not stop taking paroxetine hydrochloride extended-release tablets suddenly without talking to your doctor (unless you have symptoms of a severe allergic reaction). If you need to stop taking paroxetine hydrochloride extended-release tablets, your healthcare provider can tell you how to safely stop taking it.

What should I avoid while taking paroxetine hydrochloride extended-release tablets?

Paroxetine hydrochloride extended-release tablets can cause sleepiness or may affect your ability to make decisions, think clearly or react quickly. You should not drive, operate heavy machinery or do other dangerous activities until you know how paroxetine hydrochloride extended-release tablets affect you. Do not drink alcohol while using paroxetine hydrochloride extended-release tablets.

What are possible side effects of paroxetine hydrochloride extended-release tablets?

Paroxetine hydrochloride extended-release tablets may cause serious side effects, including all of those described in the section entitled “What is the most important information I should know about paroxetine hydrochloride extended-release tablets?”

Common possible side effects in people who take paroxetine hydrochloride extended-release tablets include:

- nausea
- sleepiness
- dizziness
- feeling anxious or trouble sleeping
- sexual problems
- sweating
- shaking
- constipation
- yawning
- blurred vision
- diarrhea
- dry mouth
- decreased appetite
- weakness

Tell your healthcare provider if you have any side effect that bothers you or that does not go away. These are not all the possible side effects of paroxetine hydrochloride extended-release tablets. For more information, ask your healthcare provider or pharmacist.

Call your doctor for medical advice about side effects. You may report side effects to the FDA at 1-800-FDA-1088 or 1-800-332-1088.

How should I store paroxetine hydrochloride extended-release tablets?

- Store paroxetine hydrochloride extended-release tablets at 20° to 25 °C (68° to 77°F). [See USP Controlled Room Temperature.]
- Keep paroxetine hydrochloride extended-release tablets away from light.
- Keep bottle of paroxetine hydrochloride extended-release tablets closed tightly.

Keep paroxetine hydrochloride extended-release tablets and all medicines out of the reach of children.

General information about paroxetine hydrochloride extended-release tablets

Medicines are sometimes prescribed for purposes other than those listed in a Medication Guide. Do not use paroxetine hydrochloride extended-release tablets for a condition for which it was not prescribed. Do not give paroxetine hydrochloride extended-release tablets to other people, even if they have the same condition. It may harm them.

This Medication Guide summarizes the most important information about paroxetine hydrochloride extended-release tablets. If you would like more information, talk with your healthcare provider. You may ask your healthcare provider or pharmacist for information about paroxetine hydrochloride extended-release tablets that is written for healthcare professionals.

For more information about paroxetine hydrochloride extended-release tablets call Mylan Pharmaceuticals Inc. at 1-877-446-3679 (1-877-4-INFO-RX).

What are the ingredients in paroxetine hydrochloride extended-release tablets?

Active ingredient: paroxetine hydrochloride

Inactive ingredients in tablets: colloidal silicon dioxide, hydroxypropyl cellulose, hypromellose, lactose monohydrate, magnesium stearate, methacrylic acid copolymer type C, microcrystalline cellulose, polydextrose, polyethylene glycol, polysorbate 80, sodium hydroxide, talc, titanium dioxide, triacetin and triethyl citrate. In addition, the 25 mg product contains the following coloring agents: D&C Red No. 30 Aluminum Lake, FD&C Blue No. 2 Aluminum Lake, FD&C Yellow No. 6 Aluminum Lake and the 37.5 mg product contains D&C Red No. 30 Aluminum Lake, FD&C Yellow No. 6 Aluminum Lake, lecithin and sodium alginate.

In addition, paroxetine hydrochloride extended-release tablets may also contain imprinting ink consisting of either black pigment and natural resin or black iron oxide and propylene glycol.

*Brand names listed are trademarks of their respective owners and are not trademarks of Mylan Pharmaceuticals Inc.

Mylan Pharmaceuticals Inc.
Morgantown, WV 26505 U.S.A.

REVISED MAY 2011
PRXT:R13mpbmt/MG:PRXT:R1mpb/MG:PRXT:R1mt

Additional barcode label applied by:
Physicians Total Care, Inc.
Tulsa, Oklahoma 74146

PACKAGE LABEL

PRINCIPAL DISPLAY PANEL - 12.5 mg

Paroxetine HCl
Extended-release
Tablets
12.5 mg*

PHARMACIST: Dispense the accompanying
Medication Guide to each patient.

Rx only 30 TABLETS

*Each enteric film-coated
tablet contains paroxetine
hydrochloride, USP
equivalent to 12.5 mg of
paroxetine.

Dispense in a tight, light-resistant
container as defined in the USP
using a child-resistant closure.

Keep container tightly closed.

Keep this and all medication
out of the reach of children.

Store at 20° to 25°C (68° to 77°F).
[See USP Controlled Room
Temperature.]

Usual Dosage: See accompanying
prescribing information.

PACKAGE LABEL

PRINCIPAL DISPLAY PANEL - 25 mg

Paroxetine HCl
Extended-release
Tablets
25 mg*

PHARMACIST: Dispense the accompanying
Medication Guide to each patient.

Rx only 30 TABLETS

*Each enteric film-coated
tablet contains paroxetine
hydrochloride, USP
equivalent to 25 mg of
paroxetine.

Dispense in a tight, light-resistant
container as defined in the USP
using a child-resistant closure.

Keep container tightly closed.

Keep this and all medication
out of the reach of children.

Store at 20° to 25°C (68° to 77°F).
[See USP Controlled Room
Temperature.]

Usual Dosage: See accompanying
prescribing information.